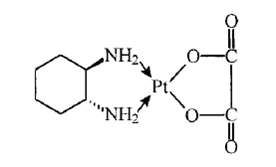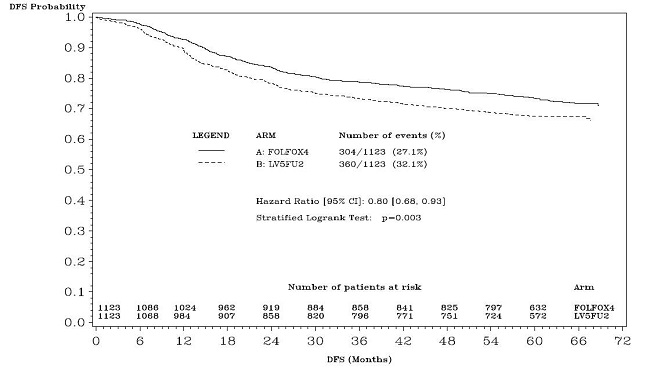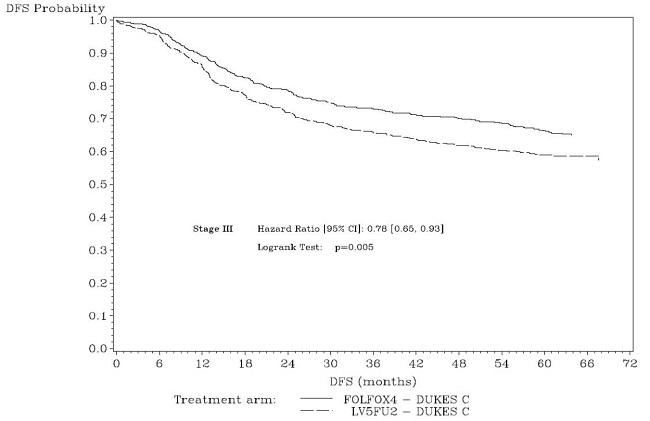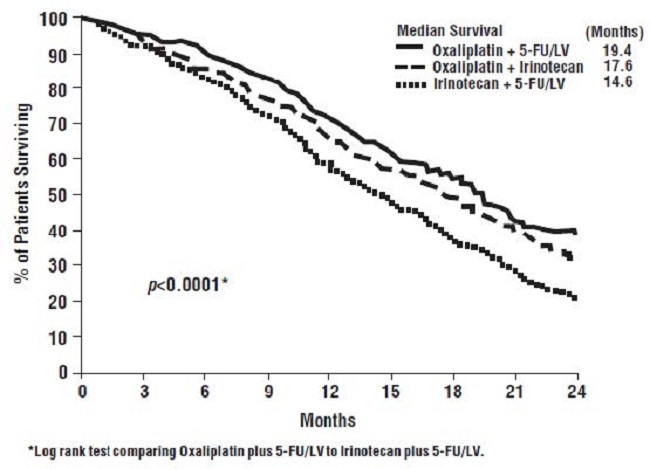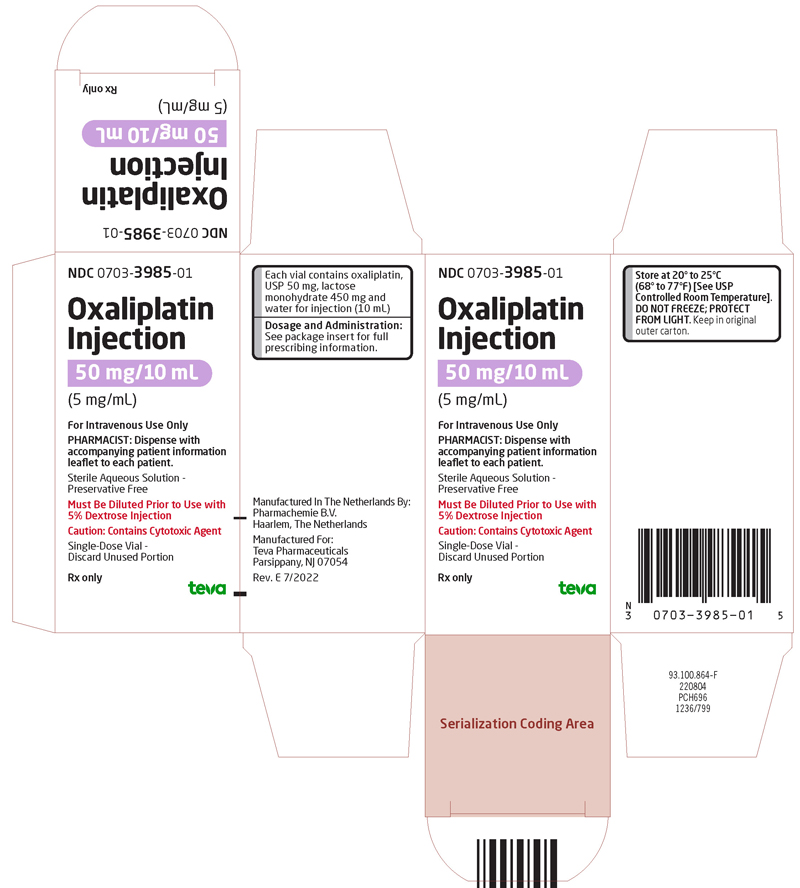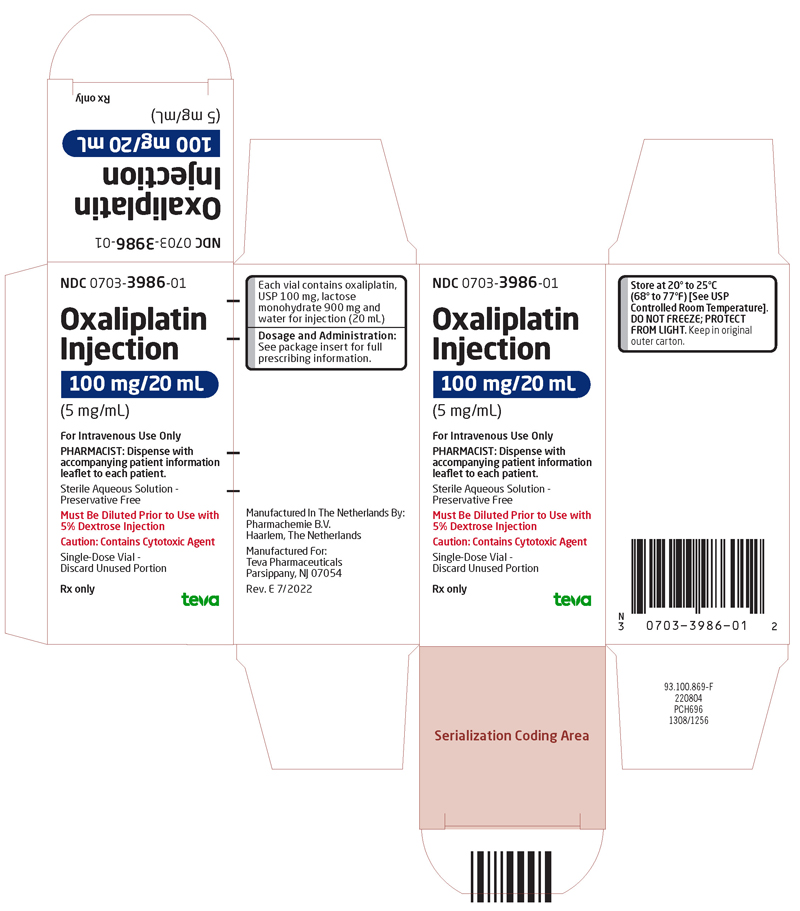 DRUG LABEL: Oxaliplatin
NDC: 0703-3985 | Form: INJECTION, SOLUTION, CONCENTRATE
Manufacturer: Teva Parenteral Medicines, Inc.
Category: prescription | Type: HUMAN PRESCRIPTION DRUG LABEL
Date: 20241028

ACTIVE INGREDIENTS: OXALIPLATIN 50 mg/10 mL
INACTIVE INGREDIENTS: WATER; LACTOSE MONOHYDRATE

HIGHLIGHTS OF PRESCRIBING INFORMATION

These highlights do not include all the information needed to use OXALIPLATIN INJECTION safely and effectively. See full prescribing information for OXALIPLATIN INJECTION.
OXALIPLATIN injection, for intravenous use
Initial U.S. Approval: 2002

WARNING: HYPERSENSITIVITY REACTIONS, INCLUDING ANAPHYLAXIS

See full prescribing information for complete boxed warning.

Serious and fatal hypersensitivity adverse reactions, including anaphylaxis, can occur with oxaliplatin within minutes of administration and during any cycle. Oxaliplatin is contraindicated in patients with hypersensitivity reactions to oxaliplatin and other platinum-based drugs. Immediately and permanently discontinue oxaliplatin for hypersensitivity reactions and administer appropriate treatment. (4, 5.1)

1 INDICATIONS AND USAGE

Oxaliplatin Injection is a platinum-based drug used in combination with infusional fluorouracil and leucovorin, which is indicated for:

- adjuvant treatment of stage III colon cancer in patients who have undergone complete resection of the primary tumor. (1)
- treatment of advanced colorectal cancer. (1)

2 DOSAGE AND ADMINISTRATION

- Administer Oxaliplatin Injection 85 mg/m^2 as an intravenous infusion over 120 minutes concurrently with leucovorin over 120 minutes in separate bags, followed by fluorouracil on Day 1 of each 14-day cycle. Administer fluorouracil and leucovorin on Day 2 as recommended. (2.1)
- Adjuvant Treatment: Continue treatment for up to 12 cycles or unacceptable toxicity. (2.1)
- Advanced Colorectal Cancer: Continue treatment until disease progression or unacceptable toxicity. (2.1)

3 DOSAGE FORMS AND STRENGTHS

Injection: 50 mg/10 mL and 100 mg/20 mL in single-dose vials. (3)

4 CONTRAINDICATIONS

- History of hypersensitivity reaction to oxaliplatin or other platinum-based drugs. (4, 5.1)

5 WARNINGS AND PRECAUTIONS

- Peripheral Sensory Neuropathy: Acute and delayed neuropathy can occur. Avoid topical application of ice. Reduce the dose or permanently discontinue Oxaliplatin Injection as recommended. (5.2)

- Severe Myelosuppression: Delay Oxaliplatin Injection until neutrophils are greater than or equal to 1.5 × 10^9/L and platelets are greater than or equal to 75 ×10^9/L. Withhold Oxaliplatin Injection for sepsis or septic shock. Dose reduce after recovery from grade 4 neutropenia, febrile neutropenia, or grade 3 to 4 thrombocytopenia as recommended. (5.3)
- Posterior Reversible Encephalopathy Syndrome (PRES): Permanently discontinue Oxaliplatin Injection in patients who develop PRES. (5.4)
- Pulmonary Toxicity: Withhold Oxaliplatin Injection until investigation excludes interstitial lung disease or pulmonary fibrosis. (5.5)
- Hepatotoxicity: Monitor liver function tests at baseline, before each subsequent cycle, and as clinically indicated. (5.6)
- QT Interval Prolongation: Avoid in patients with congenital long QT syndrome. Monitor electrocardiograms in patients with congestive heart failure, bradyarrhythmias, and electrolyte abnormalities, and in patients taking drugs known to prolong the QT interval. Correct electrolyte abnormalities prior to initiating Oxaliplatin Injection and periodically during treatment. (5.7)

- Rhabdomyolysis: Permanently discontinue Oxaliplatin Injection if rhabdomyolysis occurs. (5.8)
- Hemorrhage: Increase frequency of monitoring in patients who are receiving Oxaliplatin Injection with fluorouracil/leucovorin and oral anticoagulants (5.9)
- Embryo-Fetal Toxicity: Can cause fetal harm. Advise pregnant women of the potential risk to a fetus. Advise males and females of reproductive potential to use an effective method of contraception. (5.10, 8.1, 8.3)

6 ADVERSE REACTIONS

Most common adverse reactions (incidence greater than or equal to 40%) were peripheral sensory neuropathy, neutropenia, thrombocytopenia, anemia, nausea, increase in transaminases and alkaline phosphatase, diarrhea, emesis, fatigue, and stomatitis. (6.1)

To report SUSPECTED ADVERSE REACTIONS, contact Teva at 1-888-838-2872 or FDA at 1-800-FDA-1088 or www.fda.gov/medwatch.

8 USE IN SPECIFIC POPULATIONS

- Females: Advise female patients of reproductive potential to use effective contraception while receiving oxaliplatin and for 9 months after the final dose. (8.3)
- Males: Based on its mechanism action as a genotoxic drug, advise males with female partners of reproductive potential to use effective contraception while receiving oxaliplatin and for 6 months after the final dose [see Nonclinical Toxicology (13.1)].

FULL PRESCRIBING INFORMATION

WARNING: HYPERSENSITIVITY REACTIONS, INCLUDING ANAPHYLAXIS

Serious and fatal hypersensitivity adverse reactions, including anaphylaxis, can occur with oxaliplatin within minutes of administration and during any cycle. Oxaliplatin is contraindicated in patients with hypersensitivity reactions to oxaliplatin and other platinum-based drugs [see Contraindications (4)]. Immediately and permanently discontinue oxaliplatin for hypersensitivity reactions and administer appropriate treatment for management of the hypersensitivity reaction [see Warnings and Precautions (5.1)].

1 INDICATIONS AND USAGE

Oxaliplatin Injection, in combination with infusional fluorouracil and leucovorin, is indicated for:

- adjuvant treatment of stage III colon cancer in patients who have undergone complete resection of the primary tumor.
- treatment of advanced colorectal cancer.

2 DOSAGE AND ADMINISTRATION

2.1 Recommended Dosage

Administer Oxaliplatin Injection in combination with fluorouracil and leucovorin every 2 weeks.

- For adjuvant treatment, continue treatment for up to 12 cycles or unacceptable toxicity.
- For advanced colorectal cancer, continue treatment until disease progression or unacceptable toxicity.

Day 1
Administer Oxaliplatin Injection 85 mg/m^2 as an intravenous infusion over 120 minutes and leucovorin 200 mg/m^2 as an intravenous infusion over 120 minutes at the same time in separate bags, followed by fluorouracil 400 mg/m^2 as intravenous bolus over 2 to 4 minutes, followed by fluorouracil 600 mg/m^2 as a 22-hour continuous infusion.

Day 2

Administer leucovorin 200 mg/m^2 as an intravenous infusion over 120 minutes, followed by fluorouracil 400 mg/m^2 as intravenous bolus over 2 to 4 minutes, followed by fluorouracil 600 mg/m^2 as a 22-hour continuous infusion.

Refer to the prescribing information for fluorouracil and leucovorin for additional information.

2.2 Dose Modifications for Adverse Reactions

Prolongation of infusion time for Oxaliplatin Injection from 2 hours to 6 hours may mitigate acute toxicities, such as non–life-threatening infusion-related reactions.

Permanently discontinue Oxaliplatin Injection for any of the following:

- Hypersensitivity Reactions [see Warnings and Precautions (5.1)]
- Posterior reversible encephalopathy syndrome (PRES) [see Warnings and Precautions (5.4)]
- Confirmed interstitial lung disease or pulmonary fibrosis [see Warnings and Precautions (5.5)]
- Rhabdomyolysis [see Warnings and Precautions (5.8)]

Refer to the fluorouracil and leucovorin prescribing information for dosage modifications for adverse reactions.

Dosage Modifications for Adjuvant Treatment

Dosage modifications for adverse reactions for adjuvant treatment are presented in Table 1.

Table 1: Dosage Modifications for Adjuvant Treatment in Patients with Stage III Colon Cancer
Adverse Reactions | Severity | Oxaliplatin Injection Dosage Modifications
Peripheral Sensory Neuropathy [see Warnings and Precautions (5.2)] | Persistent Grade 2 | Consider reducing Oxaliplatin Injection dose to 75 mg/m^2.
Peripheral Sensory Neuropathy [see Warnings and Precautions (5.2)] | Persistent Grade 3 | Consider discontinuing Oxaliplatin Injection.
Peripheral Sensory Neuropathy [see Warnings and Precautions (5.2)] | Grade 4 | Discontinue Oxaliplatin Injection.
Myelosuppression; [see Warnings and Precautions (5.3), Adverse Reactions (6.1)]. | Grade 4 neutropenia or febrile neutropenia | Delay the next dose until neutrophils greater than or equal to 1.5 × 10^9/L and platelets greater than or equal to 75 × 10^9/L.; Reduce Oxaliplatin Injection dose to 75 mg/m^2.
Myelosuppression; [see Warnings and Precautions (5.3), Adverse Reactions (6.1)]. | Grade 3-4 thrombocytopenia | Delay the next dose until neutrophils greater than or equal to 1.5 × 10^9/L and platelets greater than or equal to 75 × 10^9/L.; Reduce Oxaliplatin Injection dose to 75 mg/m^2.
Gastrointestinal Adverse Reactions; [see Adverse Reactions (6.1)] | Grade 3-4 | After recovery, reduce Oxaliplatin Injection dose to 75 mg/m^2 along with a dose reduction of fluorouracil to 300 mg/m^2 as an intravenous bolus and 500 mg/m^2 as a 22-hour continuous infusion.

Dosage Modifications for Advanced Colorectal Cancer

Dosage modifications for adverse reactions for advanced colorectal cancer are presented in Table 2.

Table 2: Dosage Modifications for Advanced Colorectal Cancer
Adverse Reactions | Severity | Oxaliplatin Injection Dosage Modifications
Neuropathy [see Warnings and Precautions (5.2)] | Persistent Grade 2 | Consider reducing Oxaliplatin Injection dose to 65 mg/m^2.
Neuropathy [see Warnings and Precautions (5.2)] | Persistent Grade 3 | Consider discontinuing Oxaliplatin Injection.
Neuropathy [see Warnings and Precautions (5.2)] | Grade 4 | Discontinue Oxaliplatin Injection.
Myelosuppression [see Warnings and Precautions (5.3), Adverse Reactions (6.1)] | Grade 4 neutropenia or febrile neutropenia | Delay the next dose until neutrophils greater than or equal to 1.5 × 10^9/L and platelets greater than or equal to 75 × 10^9/L. Reduce Oxaliplatin Injection dose to 65 mg/m^2.
Myelosuppression [see Warnings and Precautions (5.3), Adverse Reactions (6.1)] | Grade 3-4 thrombocytopenia | Delay the next dose until neutrophils greater than or equal to 1.5 × 10^9/L and platelets greater than or equal to 75 × 10^9/L. Reduce Oxaliplatin Injection dose to 65 mg/m^2.
Gastrointestinal Adverse Reactions [see Adverse Reactions (6.1)] | Grade 3-4 | After recovery, reduce Oxaliplatin Injection dose to 65 mg/ m^2 along with a dose reduction of fluorouracil to 300 mg/m^2 as an intravenous bolus and 500 mg/m^2 as a 22-hour continuous infusion.

2.3 Dose Modifications for Patients with Renal Impairment

In patients with severe renal impairment (creatinine clearance [CLcr] less than 30 mL/min, calculated by the Cockcroft-Gault equation), reduce the Oxaliplatin Injection dose to 65 mg/m^2 [see Use in Specific Populations (8.6), Clinical Pharmacology (12.3)].

2.4 Preparation and Administration

- Oxaliplatin Injection is a cytotoxic drug. Follow applicable special handling and disposal procedures.^1
- Do not freeze.
- Protect the concentrated solution from light.
- Dilute concentrated solution with 250 to 500 mL of 5% Dextrose Injection, USP. Do not dilute with sodium chloride solution or other chloride-containing solutions.
- Store diluted solution for no more than 6 hours at room temperature (20°C to 25°C [68°F to 77°F]) or 24 hours under refrigeration (2°C to 8°C [36°F to 46°F]). Protection from light is not required.
- Visually inspect for particulate matter and discoloration prior to administration and discard if present.
- Do not mix Oxaliplatin Injection or administer Oxaliplatin Injection through the same infusion line concurrently with alkaline medications or media (such as basic solutions of fluorouracil).
- Flush the infusion line with 5% Dextrose Injection, USP prior to administration of any concomitant medication.
- Do not use needles or intravenous administration sets containing aluminum parts for the preparation or mixing of Oxaliplatin Injection. Aluminum has been reported to cause degradation of platinum compounds.
- Administer Oxaliplatin Injection as an intravenous infusion over 120 minutes concurrently with leucovorin over 120 minutes in separate bags.

3 DOSAGE FORMS AND STRENGTHS

Injection: 50 mg/10 mL (5 mg/mL) and 100 mg/20 mL (5 mg/mL) as a sterile, preservative-free, aqueous solution in single-dose vials.

4 CONTRAINDICATIONS

Oxaliplatin Injection is contraindicated in patients with a history of a hypersensitivity reaction to oxaliplatin or other platinum-based drugs. Reactions have included anaphylaxis [see Warnings and Precautions (5.1)].

5 WARNINGS AND PRECAUTIONS

5.1 Hypersensitivity Reactions

Serious and fatal hypersensitivity reactions, including anaphylaxis, can occur with oxaliplatin within minutes of administration and during any cycle. Grade 3-4 hypersensitivity reactions, including anaphylaxis, occurred in 2% to 3% of patients with colon cancer who received oxaliplatin. Hypersensitivity reactions, including rash, urticaria, erythema, pruritus, and rarely, bronchospasm and hypotension, were similar in nature and severity to those reported with other platinum-based drugs.

Oxaliplatin is contraindicated in patients with hypersensitivity reactions to platinum-based drugs [see Contraindications (4)]. Immediately and permanently discontinue oxaliplatin for hypersensitivity reactions and administer appropriate treatment for management of hypersensitivity reactions.

5.2 Peripheral Sensory Neuropathy

Oxaliplatin can cause acute and delayed neuropathy. Reduce the dose or permanently discontinue oxaliplatin for persistent neurosensory reactions based on the severity of the adverse reaction [see Dosage and Administration (2.2)].

Acute Neuropathy

Acute neuropathy typically presents as a reversible, primarily peripheral sensory neuropathy that occurs within hours or 2 days following a dose, resolves within 14 days, and frequently recurs with further dosing. The symptoms can be precipitated or exacerbated by exposure to cold temperature or cold objects and they usually present as transient paresthesia, dysesthesia and hypoesthesia in the hands, feet, perioral area, or throat. Jaw spasm, abnormal tongue sensation, dysarthria, eye pain, and a feeling of chest pressure have also been observed. The acute, reversible pattern of sensory neuropathy was observed in about 56% of patients who received oxaliplatin with fluorouracil/leucovorin. In any individual cycle, acute neuropathy occurred in approximately 30% of patients. For grade 3 peripheral sensory neuropathy, the median time to onset was 9 cycles for adjuvant treatment and 6 cycles for previously treated advanced colorectal cancer.

An acute syndrome of pharyngolaryngeal dysesthesia occurred in 1% to 2% (grade 3-4) of patients previously untreated for advanced colorectal cancer. Subjective sensations of dysphagia or dyspnea, without any laryngospasm or bronchospasm (no stridor or wheezing) occurred in patients previously treated for advanced colorectal cancer.

Avoid topical application of ice for mucositis prophylaxis or other conditions, because cold temperature can exacerbate acute neurological symptoms.

Delayed Neuropathy

Delayed neuropathy typically presents as a persistent (greater than 14 days), primarily peripheral sensory neuropathy that is usually characterized by paresthesias, dysesthesias, and hypoesthesias, but may also include deficits in proprioception that can interfere with daily activities (e.g., writing, buttoning, swallowing, and difficulty walking from impaired proprioception). These forms of neuropathy occurred in 48% of patients receiving oxaliplatin. Delayed neuropathy can occur without any prior acute neuropathy. Most patients (80%) who developed grade 3 persistent neuropathy progressed from prior grade 1 or 2 reactions. These symptoms may improve in some patients upon discontinuation of oxaliplatin.

Adjuvant treatment

In the adjuvant treatment trial, neuropathy was graded using NCI CTC, version 1 as summarized in Table 3.

Table 3: Grading for Neuropathy in Adjuvant Treatment Trial
Grade | Definition
0 | No change or none
1 | Mild paresthesias, loss of deep tendon reflexes
2 | Mild or moderate objective sensory loss, moderate paresthesias
3 | Severe objective sensory loss or paresthesias that interfere with function
4 | Not applicable

Peripheral sensory neuropathy occurred in 92% of patients (all grades), including 13% of patients (grade 3) who received oxaliplatin with fluorouracil/leucovorin. At the 28-day follow-up after the last treatment cycle, 60% of patients had any grade (grade 1=40%, grade 2=16%, grade 3=5%) peripheral sensory neuropathy, decreasing to 39% at 6 months of follow-up (grade 1=31%, grade 2=7%, grade 3=1%) and 21% at 18 months of follow-up (grade 1=17%, grade 2=3%, grade 3=1%).

Advanced colorectal cancer

In the advanced colorectal cancer trials, neuropathy was graded using the neurotoxicity scale summarized in Table 4.

Table 4: Grading for Neuropathy in Advanced Colorectal Cancer Trials
Grade | Definition
1 | Resolved and did not interfere with functioning
2 | Interfered with function but not daily activities
3 | Pain or functional impairment that interfered with daily activities
4 | Persistent impairment that is disabling or life-threatening

Neuropathy occurred in 82% (all grades) of patients previously untreated for advanced colorectal cancer, including 19% grade 3-4; and in 74% (all grades) of patients previously treated for advanced colorectal cancer, including 7% grade 3-4.

5.3 Severe Myelosuppression

Grade 3 or 4 neutropenia occurred in 41% to 44% of patients with colorectal cancer who received oxaliplatin with fluorouracil/leucovorin. Sepsis, neutropenic sepsis and septic shock, including fatal outcomes, occurred in patients who received oxaliplatin [see Adverse Reactions (6.1, 6.2)].

Grade 3 or 4 thrombocytopenia occurred in 2% to 5% of patients with colorectal cancer who received oxaliplatin with fluorouracil/leucovorin.

Monitor complete blood cell count at baseline, before each subsequent cycle and as clinically indicated. Delay Oxaliplatin Injection until neutrophils are greater than or equal to 1.5 × 10^9/L and platelets are greater than or equal to 75 × 10^9/L. Withhold Oxaliplatin Injection for sepsis or septic shock. Dose reduce Oxaliplatin Injection after recovery from grade 4 neutropenia, febrile neutropenia or grade 3-4 thrombocytopenia as recommended [see Dosage and Administration (2.2)].

5.4 Posterior Reversible Encephalopathy Syndrome

PRES occurred in less than 0.1% of patients across clinical trials [see Adverse Reactions (6.1)]. Signs and symptoms of PRES can include headache, altered mental functioning, seizures, abnormal vision from blurriness to blindness, associated or not with hypertension. Confirm the diagnosis of PRES with magnetic resonance imaging. Permanently discontinue Oxaliplatin Injection in patients who develop PRES.

5.5 Pulmonary Toxicity

Oxaliplatin has been associated with pulmonary fibrosis (less than 1% of patients), which may be fatal [see Adverse Reactions (6.1)].

In the adjuvant treatment trial, the combined incidence of cough and dyspnea was 7.4% (any grade), including less than 1% (grade 3) in the oxaliplatin arm. One patient died from eosinophilic pneumonia in the oxaliplatin arm.

In the previously untreated advanced colorectal cancer trial, the combined incidence of cough, dyspnea, and hypoxia was 43% (any grade), including 7% (grade 3-4) in the oxaliplatin with fluorouracil/leucovorin arm.

In case of unexplained respiratory symptoms, such as non-productive cough, dyspnea, crackles, or radiological pulmonary infiltrates, withhold Oxaliplatin Injection until further pulmonary investigation excludes interstitial lung disease or pulmonary fibrosis. Permanently discontinue Oxaliplatin Injection for confirmed interstitial lung disease or pulmonary fibrosis.

5.6 Hepatotoxicity

In the adjuvant treatment trial, increased transaminases (57% vs 34%) and alkaline phosphatase (42% vs 20%) occurred more commonly in the oxaliplatin arm than in the fluorouracil/leucovorin arm [see Adverse Reactions (6.1)]. The incidence of increased bilirubin was similar on both arms. Changes noted on liver biopsies include: peliosis, nodular regenerative hyperplasia or sinusoidal alterations, perisinusoidal fibrosis, and veno-occlusive lesions.

Consider evaluating patients who develop abnormal liver tests or portal hypertension, which cannot be explained by liver metastases, for hepatic vascular disorders. Monitor liver function tests at baseline, before each subsequent cycle, and as clinically indicated.

5.7 QT Interval Prolongation and Ventricular Arrhythmias

QT prolongation and ventricular arrhythmias, including fatal torsade de pointes, have been reported with oxaliplatin [see Adverse Reactions (6.2)].

Avoid Oxaliplatin Injection in patients with congenital long QT syndrome. Monitor electrocardiograms (ECG) in patients with congestive heart failure, bradyarrhythmias, and electrolyte abnormalities and in patients taking drugs known to prolong the QT interval, including Class Ia and III antiarrhythmics [see Drug Interactions (7.1)]. Monitor and correct electrolyte abnormalities prior to initiating Oxaliplatin Injection and periodically during treatment.

5.8 Rhabdomyolysis

Rhabdomyolysis, including fatal cases, has been reported with oxaliplatin [see Adverse Reactions (6.2)]. Permanently discontinue Oxaliplatin Injection for any signs or symptoms of rhabdomyolysis.

5.9 Hemorrhage

The incidence of hemorrhage in clinical trials was higher on the oxaliplatin combination arm compared to the fluorouracil/leucovorin arm. These reactions included gastrointestinal bleeding, hematuria, and epistaxis. In the adjuvant treatment trial, 2 patients died from intracerebral hemorrhage [see Adverse Reactions (6.1)].

Prolonged prothrombin time and INR occasionally associated with hemorrhage have been reported in patients who received oxaliplatin with fluorouracil/leucovorin while on anticoagulants [see Adverse Reactions (6.2)]. Increase frequency of monitoring in patients who are receiving Oxaliplatin Injection with fluorouracil/leucovorin and oral anticoagulants [see Drug Interactions (7.3)].

Thrombocytopenia and immune-mediated thrombocytopenia have been observed with oxaliplatin. Rapid onset of thrombocytopenia and greater risk of bleeding have been observed in immune-mediated thrombocytopenia. In this case, consider discontinuing Oxaliplatin Injection.

5.10 Embryo-Fetal Toxicity

Based on findings from animal studies and its mechanism of action, Oxaliplatin Injection can cause fetal harm when administered to a pregnant woman. The available human data do not establish the presence or absence of major birth defects or miscarriage related to the use of oxaliplatin. Reproductive toxicity studies demonstrated adverse effects on embryo-fetal development in rats at maternal doses that were below the recommended human dose based on body surface area. Advise pregnant women of the potential risk to a fetus.

Advise females of reproductive potential to use effective contraception during treatment with Oxaliplatin Injection and for 9 months after the final dose. Advise males with female partners of reproductive potential to use effective contraception during treatment with Oxaliplatin Injection and for 6 months after the final dose [see Use in Specific Populations (8.1, 8.3)].

6 ADVERSE REACTIONS

The following clinically significant adverse reactions are described elsewhere in labeling:

- Hypersensitivity Reactions [see Warnings and Precautions (5.1)]
- Peripheral Sensory Neuropathy [see Warnings and Precautions (5.2)]
- Severe Myelosuppression [see Warnings and Precautions (5.3)]
- Reversible Posterior Leukoencephalopathy Syndrome [see Warnings and Precautions (5.4)]
- Pulmonary Toxicity [see Warnings and Precautions (5.5)]
- Hepatotoxicity [see Warnings and Precautions (5.6)]
- QT Interval Prolongation and Ventricular Arrhythmias [see Warnings and Precautions (5.7)]
- Rhabdomyolysis [see Warnings and Precautions (5.8)]
- Hemorrhage [see Warnings and Precautions (5.9)]

6.1 Clinical Trials Experience

Because clinical trials are conducted under widely varying conditions, adverse reaction rates observed in the clinical trials of a drug cannot be directly compared to rates in the clinical trials of another drug and may not reflect the rates observed in practice.

More than 1100 patients with stage II or III colon cancer and more than 4,000 patients with advanced colorectal cancer were treated in trials with oxaliplatin. The most common adverse reactions in patients with stage II or III colon cancer receiving adjuvant treatment were peripheral sensory neuropathy, neutropenia, thrombocytopenia, anemia, nausea, increase in transaminases and alkaline phosphatase, diarrhea, emesis, fatigue and stomatitis. The most common adverse reactions in previously untreated and treated patients with advanced colorectal cancer were peripheral sensory neuropathies, fatigue, neutropenia, nausea, emesis, and diarrhea.

Adjuvant Treatment

The safety of oxaliplatin in combination with fluorouracil (FU)/leucovorin (LV) was evaluated in patients with stage II or III colon cancer, who had undergone complete resection of the primary tumor in the adjuvant treatment trial [see Clinical Studies (14.1)].

Fatal adverse reactions in patients who received oxaliplatin in the combination arm included sepsis/neutropenic sepsis (n=3), intracerebral hemorrhage (n=2), and eosinophilic pneumonia (n=1).

Thromboembolic events occurred in 6% (grade 3-4, 1.2%) of patients in the oxaliplatin arm.

Grade 3 or 4 adverse reactions occurred in 70% of patients in the oxaliplatin arm. Grade 3-4 gastrointestinal bleeding occurred in 0.2% of patients. Febrile neutropenia occurred in 0.7% and documented infection with concomitant grade 3-4 neutropenia occurred in 1.1%.

Discontinuation due to an adverse reaction occurred in 15% of the patients in the oxaliplatin arm.

Tables 5, 6, and 7 summarize the adverse reactions reported in patients with colon cancer receiving adjuvant treatment.

Table 5: Adverse Reactions Reported in Patients with Colon Cancer Receiving Adjuvant Treatment (greater than or equal to 5% of all patients and with greater than or equal to 1% grade 3-4)
Adverse Reaction* | Oxaliplatin+ FU/LV N=1108 |  | FU/LV N=1111
Adverse Reaction* | All Grades (%) | Grade 3-4 (%) | All Grades (%) | Grade 3-4 (%)
Neurology
Peripheral Sensory Neuropathy | 92 | 12 | 16 | <1
Gastrointestinal
Nausea | 74 | 5 | 61 | 2
Diarrhea | 56 | 11 | 48 | 7
Vomiting | 47 | 6 | 24 | 1
Stomatitis | 42 | 3 | 40 | 2
Anorexia | 13 | 1 | 8 | <1
Constitutional Symptoms/Pain
Fatigue | 44 | 4 | 38 | 1
Abdominal Pain | 18 | 1 | 17 | 2
Dermatology/Skin
Skin Disorder | 32 | 2 | 36 | 2
Injection Site Reaction† | 11 | 3 | 10 | 3
Fever/Infection
Fever | 27 | 1 | 12 | 1
Infection | 25 | 4 | 25 | 3
Allergy/Immunology
Allergic Reaction | 10 | 3 | 2 | <1
* Event coded in WHO-ART dictionary
† Includes thrombosis related to the catheter

Table 6: Adverse Reactions Reported in Patients with Colon Cancer Receiving Adjuvant Treatment (greater than or equal to 5% of all patients but with less than 1% grade 3-4)
Adverse Reaction* | Oxaliplatin+ FU/LV N=1108 | FU/LV N=1111
Adverse Reaction* | All Grades (%) | All Grades (%)
Dermatology/Skin
Alopecia† | 30 | 28
Gastrointestinal
Constipation | 22 | 19
Taste Perversion | 12 | 8
Dyspepsia | 8 | 5
Constitutional Symptoms/Pain/Ocular/Visual
Epistaxis | 16 | 12
Weight Increase | 10 | 10
Conjunctivitis | 9 | 15
Headache | 7 | 5
Dyspnea | 5 | 3
Pain | 5 | 5
Abnormal Lacrimation | 4 | 12
Neurology
Sensory Disturbance | 8 | 1
Allergy/Immunology
Rhinitis | 6 | 8
* Event coded in WHO-ART dictionary
† No complete alopecia was reported

In females, the following grade 3-4 adverse reactions were more frequent: diarrhea, fatigue, neutropenia, nausea, and vomiting.

In patients greater than or equal to 65 years old, the incidence of grade 3-4 diarrhea and neutropenia was higher than in younger adults.

Clinically relevant adverse reactions were reported in greater than or equal to 2% and less than 5% of the patients in the oxaliplatin arm (listed in decreasing order of frequency) were pain, leukopenia, weight loss, and cough.

Table 7: Laboratory-Related Adverse Reactions Occurring in ≥5% of Patients with Colon Cancer Receiving Adjuvant Treatment
Laboratory-Related Adverse Reaction | Oxaliplatin with FU/LV N=1108 |  | FU/LV N=1111
Laboratory-Related Adverse Reaction | All Grades (%) | Grades 3-4 (%) | All Grades (%) | Grades 3-4 (%)
Hematology
Neutropenia | 79 | 41 | 40 | 5
Thrombocytopenia | 77 | 2 | 19 | <1
Anemia | 76 | 1 | 67 | <1
Hepatic
Increased Transaminases | 57 | 2 | 34 | 1
Increased Alkaline Phosphatase | 42 | <1 | 20 | <1
Hyperbilirubinemia | 20 | 4 | 20 | 5

Previously Untreated Advanced Colorectal Cancer

The safety of oxaliplatin in combination with fluorouracil (FU)/leucovorin (LV) was evaluated in a randomized trial of patients with previously untreated advanced colorectal cancer [see Clinical Studies (14.2)]. The adverse reaction profile in this trial was similar to that seen in other trials.

Tables 8, 9, and 10 summarize the adverse reactions reported in the previously untreated advanced colorectal cancer trial.

Table 8: Adverse Reactions Reported in Patients in the Previously Untreated Advanced Colorectal Cancer Clinical Trial (greater than or equal to 5% of all patients and with greater than or equal to 1% grade 3-4)
Adverse Reaction* | Oxaliplatin+ FU/LV N=259 |  | Irinotecan + FU/LV N=256 |  | Oxaliplatin+ Irinotecan N=258
Adverse Reaction* | All Grades (%) | Grades 3-4 (%) | All Grades (%) | Grades 3-4 (%) | All Grades (%) | Grades 3-4 (%)
Neurology
Neuropathy | 82 | 19 | 18 | 2 | 69 | 7
Paresthesias | 77 | 18 | 16 | 2 | 62 | 6
Pharyngo-laryngeal Dysesthesias | 38 | 2 | 1 | 0 | 28 | 1
Neuro-sensory | 12 | 1 | 2 | 0 | 9 | 1
Neuro NOS† | 1 | 0 | 1 | 0 | 1 | 0
Gastrointestinal
Nausea | 71 | 6 | 67 | 15 | 83 | 19
Diarrhea | 56 | 12 | 65 | 29 | 76 | 25
Vomiting | 41 | 4 | 43 | 13 | 64 | 23
Stomatitis | 38 | 0 | 25 | 1 | 19 | 1
Anorexia | 35 | 2 | 25 | 4 | 27 | 5
Constipation | 32 | 4 | 27 | 2 | 21 | 2
Diarrhea-colostomy | 13 | 2 | 16 | 7 | 16 | 3
Gastrointestinal NOS† | 5 | 2 | 4 | 2 | 3 | 2
Constitutional Symptoms/Pain/Ocular/Visual
Fatigue | 70 | 7 | 58 | 11 | 66 | 16
Abdominal Pain | 29 | 8 | 31 | 7 | 39 | 10
Myalgia | 14 | 2 | 6 | 0 | 9 | 2
Pain | 7 | 1 | 5 | 1 | 6 | 1
Abnormal Vision | 5 | 0 | 2 | 1 | 6 | 1
Neuralgia | 5 | 0 | 0 | 0 | 2 | 1
Pulmonary
Cough | 35 | 1 | 25 | 2 | 17 | 1
Dyspnea | 18 | 7 | 14 | 3 | 11 | 2
Hiccups | 5 | 1 | 2 | 0 | 3 | 2
Hepatic/Metabolic/Laboratory/Renal
Hyperglycemia | 14 | 2 | 11 | 3 | 12 | 3
Hypokalemia | 11 | 3 | 7 | 4 | 6 | 2
Dehydration | 9 | 5 | 16 | 11 | 14 | 7
Hypoalbuminemia | 8 | 0 | 5 | 2 | 9 | 1
Hyponatremia | 8 | 2 | 7 | 4 | 4 | 1
Urinary Frequency | 5 | 1 | 2 | 1 | 3 | 1
Hematology/Infection
Infection Normal ANC‡ | 10 | 4 | 5 | 1 | 7 | 2
Infection Low ANC‡ | 8 | 8 | 12 | 11 | 9 | 8
Lymphopenia | 6 | 2 | 4 | 1 | 5 | 2
Febrile Neutropenia | 4 | 4 | 15 | 14 | 12 | 11
Dermatology/Skin
Hand/Foot Syndrome | 7 | 1 | 2 | 1 | 1 | 0
Injection Site Reaction | 6 | 0 | 1 | 0 | 4 | 1
Cardiovascular
Thrombosis | 6 | 5 | 6 | 6 | 3 | 3
Hypotension | 5 | 3 | 6 | 3 | 4 | 3
* Event coded in WHO-ART dictionary
† Not otherwise specified
‡ Absolute neutrophil count

Table 9: Adverse Reactions Reported in Patients in the Previously Untreated Advanced Colorectal Cancer Clinical Trial (greater than or equal to 5% of all patients but with less than 1% grade 3-4)
Adverse Reaction* | Oxaliplatin+ FU/LV; N=259 | Irinotecan + FU/LV; N=256 | Oxaliplatin+; Irinotecan N=258
Adverse Reaction* | All Grades (%) | All Grades (%) | All Grades (%)
Dermatology/Skin
Alopecia† | 38 | 44 | 67
Flushing | 7 | 2 | 5
Pruritus | 6 | 4 | 2
Dry Skin | 6 | 2 | 5
Hematology/Infection
Fever Normal ANC‡ | 16 | 9 | 9
Cardiovascular
Edema | 15 | 13 | 10
Gastrointestinal
Taste Perversion | 14 | 6 | 8
Dyspepsia | 12 | 7 | 5
Flatulence | 9 | 6 | 5
Mouth Dryness | 5 | 2 | 3
Constitutional Symptoms/Pain/Ocular/Visual
Headache | 13 | 6 | 9
Weight Loss | 11 | 9 | 11
Epistaxis | 10 | 2 | 2
Tearing | 9 | 1 | 2
Rigors | 8 | 2 | 7
Dysphasia | 5 | 3 | 3
Sweating | 5 | 6 | 12
Arthralgia | 5 | 5 | 8
Neurology
Insomnia | 13 | 9 | 11
Depression | 9 | 5 | 7
Dizziness | 8 | 6 | 10
Anxiety | 5 | 2 | 6
Allergy/Immunology
Rash | 11 | 4 | 7
Rhinitis Allergic | 10 | 6 | 6
Hepatic/Metabolic/Laboratory/Renal
Hypocalcemia | 7 | 5 | 4
Elevated Creatinine | 4 | 4 | 5
* Event coded in WHO-ART dictionary
† No complete alopecia was reported
‡ Absolute neutrophil count

Clinically relevant adverse reactions that occurred in greater than or equal to 2% and less than 5% of the patients in the oxaliplatin and fluorouracil/leucovorin combination arm (listed in decreasing order of frequency) were: metabolic, pneumonitis, catheter infection, vertigo, prothrombin time, pulmonary, rectal bleeding, dysuria, nail changes, chest pain, rectal pain, syncope, hypertension, hypoxia, unknown infection, bone pain, pigmentation changes, and urticaria.

Table 10: Laboratory-Related Adverse Reactions Occurring in ≥5% of Patients in the Previously Untreated Advanced Colorectal Cancer Trial
Laboratory-Related Adverse Reaction | Oxaliplatin and FU/LV; N=259 |  | Irinotecan and FU/LV; N=256 |  | Oxaliplatin and; Irinotecan; N=258
Laboratory-Related Adverse Reaction | All Grades; (%) | Grades 3-4; (%) | All Grades; (%) | Grades 3-4; (%) | All Grades; (%) | Grades 3-4; (%)
Hematology
Leukopenia | 85 | 20 | 84 | 23 | 76 | 24
Neutropenia | 81 | 53 | 77 | 44 | 71 | 36
Thrombocytopenia | 71 | 5 | 26 | 2 | 44 | 4
Anemia | 27 | 3 | 28 | 4 | 25 | 3
Hepatic
Increased AST* | 17 | 1 | 2 | 1 | 11 | 1
Increased Alkaline Phosphatase | 16 | 0 | 8 | 0 | 14 | 2
Hyperbilirubinemia | 6 | 1 | 3 | 1 | 3 | 2
Increased ALT† | 6 | 1 | 2 | 0 | 5 | 2
* Aspartate transaminase
† Alanine transaminase

Previously Treated Advanced Colorectal Cancer

The safety of oxaliplatin in combination with fluorouracil (FU)/leucovorin (LV) was evaluated in a randomized trial in patients with refractory and relapsed colorectal cancer [see Clinical Studies (14.3)]. The adverse reaction profile in this trial was similar to that seen in other trials.

Three patients who received oxaliplatin in the combination arm experienced fatal adverse reactions: gastrointestinal bleeding and dehydration.

Grade 3 and 4 neutropenia were reported in 27% and 17% of patients, respectively, in the oxaliplatin with fluorouracil/leucovorin combination arm. Grade 3-4 increased serum creatinine occurred in 1% of patients in the oxaliplatin with combination fluorouracil/leucovorin arm.

Thirteen percent of patients in the oxaliplatin with fluorouracil/leucovorin combination arm discontinued treatment; the most frequent reasons were gastrointestinal adverse reactions, hematologic adverse reactions and neuropathies.

Tables 11, 12, and 13 summarize the adverse reactions reported in the previously treated advanced colorectal cancer trial.

Table 11: Adverse Reactions Reported in Patients in the Previously Treated Advanced Colorectal Cancer Trial (greater than or equal to 5% of all patients and with greater than or equal to 1% grade 3-4)
Adverse Reaction* | Oxaliplatin+ FU/LV N=150 |  | Oxaliplatin N=153 |  | FU/LV N=142
Adverse Reaction* | All Grades; (%) | Grades 3-4; (%) | All Grades; (%) | Grades 3-4; (%) | All Grades; (%) | Grades 3-4; (%)
Neurology
Neuropathy | 74 | 7 | 76 | 7 | 17 | 0
Acute | 56 | 2 | 65 | 5 | 10 | 0
Persistent | 48 | 6 | 43 | 3 | 9 | 0
Constitutional Symptoms/Pain
Fatigue | 68 | 7 | 61 | 9 | 52 | 6
Back Pain | 19 | 3 | 11 | 0 | 16 | 4
Pain | 15 | 2 | 14 | 3 | 9 | 3
Gastrointestinal
Diarrhea | 67 | 11 | 46 | 4 | 44 | 3
Nausea | 65 | 11 | 64 | 4 | 59 | 4
Vomiting | 40 | 9 | 37 | 4 | 27 | 4
Stomatitis | 37 | 3 | 14 | 0 | 32 | 3
Abdominal Pain | 33 | 4 | 31 | 7 | 31 | 5
Anorexia | 29 | 3 | 20 | 2 | 20 | 1
Gastroesophageal Reflux | 5 | 2 | 1 | 0 | 3 | 0
Hematology/Infection
Fever | 29 | 1 | 25 | 1 | 23 | 1
Febrile Neutropenia | 6 | 6 | 0 | 0 | 1 | 1
Cardiovascular
Dyspnea | 20 | 4 | 13 | 7 | 11 | 2
Coughing | 19 | 1 | 11 | 0 | 9 | 0
Edema | 15 | 1 | 10 | 1 | 13 | 1
Thromboembolism | 9 | 8 | 2 | 1 | 4 | 2
Chest Pain | 8 | 1 | 5 | 1 | 4 | 1
Dermatology/Skin
Injection Site Reaction | 10 | 3 | 9 | 0 | 5 | 1
Hepatic/Metabolic/Laboratory/Renal
Hypokalemia | 9 | 4 | 3 | 2 | 3 | 1
Dehydration | 8 | 3 | 5 | 3 | 6 | 4
* Event coded in WHO-ART dictionary

Table 12: Adverse Reactions Reported in Patients in the Previously Treated Advanced Colorectal Cancer Clinical Trial (greater than or equal to 5% of all patients but with less than 1% grade 3-4)
Adverse Reaction* | Oxaliplatin+ FU/LV; N=150 | Oxaliplatin N=153 | FU/LV N=142
Adverse Reaction* | All Grades (%) | All Grades (%) | All Grades (%)
Gastrointestinal
Constipation | 32 | 31 | 23
Dyspepsia | 14 | 7 | 10
Taste Perversion | 13 | 5 | 1
Mucositis | 7 | 2 | 10
Flatulence | 5 | 3 | 6
Constitutional Symptoms/Pain/Ocular/Visual
Headache | 17 | 13 | 8
Arthralgia | 10 | 7 | 10
Epistaxis | 9 | 2 | 1
Abnormal Lacrimation | 7 | 1 | 6
Rigors | 7 | 9 | 6
Allergy/Immunology
Rhinitis | 15 | 6 | 4
Allergic Reaction | 10 | 3 | 1
Rash | 9 | 5 | 5
Neurology
Dizziness | 13 | 7 | 8
Insomnia | 9 | 11 | 4
Dermatology/Skin
Hand-Foot Syndrome | 11 | 1 | 13
Flushing | 10 | 3 | 2
Alopecia† | 7 | 3 | 3
Pulmonary
Upper Respiratory Tract Infection | 10 | 7 | 4
Pharyngitis | 9 | 2 | 10
Cardiovascular
Peripheral Edema | 10 | 5 | 11
Hepatic/Metabolic/Laboratory/Renal
Hematuria | 6 | 0 | 4
Dysuria | 6 | 1 | 1
* Event coded in WHO-ART dictionary
† No complete alopecia was reported

Clinically relevant adverse reactions in greater than or equal to 2% and less than 5% of the patients in the oxaliplatin and fluorouracil/leucovorin combination arm (listed in decreasing order of frequency) were: anxiety, myalgia, erythematous rash, increased sweating, conjunctivitis, weight decrease, dry mouth, rectal hemorrhage, depression, ataxia, ascites, hemorrhoids, muscle weakness, nervousness, tachycardia, abnormal micturition frequency, dry skin, pruritus, hemoptysis, purpura, vaginal hemorrhage, melena, somnolence, pneumonia, proctitis, involuntary muscle contractions, intestinal obstruction, gingivitis, tenesmus, hot flashes, enlarged abdomen, and urinary incontinence.

Table 13: Laboratory-Related Adverse Reactions Occurring in ≥5% of Patients with Previously Treated Advanced Colorectal Cancer
Laboratory-Related Adverse Reaction | Oxaliplatin and FU/LV N=150 |  | Oxaliplatin N=153 |  | FU/LV N=142
Laboratory-Related Adverse Reaction | All Grades; (%) | Grades 3-4; (%) | All Grades; (%) | Grades 3-4; (%) | All Grades; (%) | Grades 3-4; (%)
Hematology
Anemia | 81 | 2 | 64 | 1 | 68 | 2
Leukopenia | 76 | 19 | 13 | 0 | 34 | 1
Neutropenia | 73 | 44 | 7 | 0 | 25 | 5
Thrombocytopenia | 64 | 4 | 30 | 3 | 20 | 0
Hepatic
Increased ALT* | 31 | 0 | 36 | 1 | 28 | 3
Increased AST† | 47 | 0 | 54 | 4 | 39 | 2
Increased Bilirubin | 13 | 1 | 13 | 5 | 22 | 6
* Alanine transaminase
† Aspartate transaminase

Additional Adverse Reactions

The following adverse reactions were observed across clinical trials.

Intravenous site reactions

Injection site reaction, including redness, swelling, and pain, can occur with oxaliplatin. In some cases, skin necrosis has occurred with extravasation.

PRES

PRES occurred in less than 0.1% of patients.

Pulmonary fibrosis and interstitial lung disease

Pulmonary fibrosis, which may be fatal, occurred in less than 1% of patients.

6.2 Postmarketing Experience

The following adverse reactions have been identified during post-approval use of oxaliplatin. Because these reactions are reported voluntarily from a population of uncertain size, it is not always possible to reliably estimate their frequency or establish a causal relationship to drug exposure.

- General: angioedema, anaphylactic shock
- Cardiovascular: QT prolongation leading to ventricular arrhythmias, including fatal torsade de pointes; bradyarrhythmia
- Neurological: loss of deep tendon reflexes, dysarthria, Lhermitte’s sign, cranial nerve palsies, fasciculations, convulsion
- Hearing and vestibular system: deafness
- Infections: septic shock, including fatal outcomes
- Infusion-related reactions and hypersensitivity reactions: laryngospasm
- Hepatic and gastrointestinal: severe diarrhea/vomiting resulting in hypokalemia, colitis (including Clostridium difficile diarrhea), metabolic acidosis, ileus, intestinal obstruction, pancreatitis, sinusoidal obstruction syndrome, perisinusoidal fibrosis which rarely may progress, focal nodular hyperplasia, esophagitis
- Musculoskeletal and connective tissue: rhabdomyolysis, including fatal outcomes
- Platelet, bleeding, and clotting disorders: immuno-allergic thrombocytopenia, prolonged prothrombin time and INR in patients receiving anticoagulants
- Blood disorders: secondary leukemia
- Red blood cell: hemolytic uremic syndrome, immuno-allergic hemolytic anemia
- Renal: acute tubular necrosis, acute interstitial nephritis, acute renal failure
- Respiratory: interstitial lung diseases (sometimes fatal) and pneumonia (including fatal outcomes)
- Vision: decrease of visual acuity, visual field disturbance, optic neuritis and transient vision loss (reversible following treatment discontinuation)
- Injury, poisoning, and procedural complications: fall-related injuries

7 DRUG INTERACTIONS

7.1 Drugs that Prolong the QT Interval

QT interval prolongation and ventricular arrhythmias can occur with oxaliplatin [see Warnings and Precautions (5.7)]. Avoid coadministration of oxaliplatin with medicinal products with a known potential to prolong the QT interval.

7.2 Use with Nephrotoxic Products

Because platinum-containing species are eliminated primarily through the kidney, clearance of these products may be decreased by coadministration of potentially nephrotoxic compounds [see Clinical Pharmacology (12.3)]. Avoid coadministration of oxaliplatin with medicinal products known to cause nephrotoxicity.

7.3 Use with Anticoagulants

Prolonged prothrombin time and INR occasionally associated with hemorrhage have been reported in patients who received oxaliplatin with fluorouracil/leucovorin while on anticoagulants [see Warnings and Precautions (5.9), Adverse Reactions (6.2)]. Increase frequency of monitoring in patients who are receiving oxaliplatin with fluorouracil/leucovorin and oral anticoagulants.

8 USE IN SPECIFIC POPULATIONS

8.1 Pregnancy

Risk Summary

Based on its direct interaction with DNA, Oxaliplatin Injection can cause fetal harm when administered to a pregnant woman. The available human data do not establish the presence or absence of major birth defects or miscarriage related to the use of oxaliplatin. Reproductive toxicity studies demonstrated adverse effects on embryo-fetal development in rats at maternal doses that were below the recommended human dose based on body surface area (see Data). Advise a pregnant woman of the potential risk to a fetus.

In the U.S. general population, the estimated background risk of major birth defects and miscarriage in clinically recognized pregnancies is 2% to 4% and 15% to 20%, respectively.

Data

Animal data

Pregnant rats were administered oxaliplatin at less than one-tenth the recommended human dose based on body surface area during gestation days (GD) 1 to 5 (preimplantation), GD 6 to 10, or GD 11 to 16 (during organogenesis). Oxaliplatin caused developmental mortality (increased early resorptions) when administered on days GD 6 to 10 and GD 11 to 16 and adversely affected fetal growth (decreased fetal weight, delayed ossification) when administered on days GD 6 to 10.

8.2 Lactation

Risk Summary

There are no data on the presence of oxaliplatin or its metabolites in human or animal milk or its effects on the breastfed infant or on milk production. Because of the potential for serious adverse reactions in breastfed infants, advise women not to breastfeed during treatment with Oxaliplatin Injection and for 3 months after the final dose.

8.3 Females and Males of Reproductive Potential

Pregnancy Testing

Verify pregnancy status in females of reproductive potential prior to initiating Oxaliplatin Injection [see Use in Specific Populations (8.1)].

Contraception

Oxaliplatin Injection can cause embryo-fetal harm when administered to a pregnant woman [see Use in Specific Populations (8.1)].

Females

Advise female patients of reproductive potential to use effective contraception while receiving Oxaliplatin Injection and for 9 months after the final dose.

Males

Based on its mechanism action as a genotoxic drug, advise males with female partners of reproductive potential to use effective contraception while receiving Oxaliplatin Injection and for 6 months after the final dose [see Nonclinical Toxicology (13.1)].

Infertility

Based on animal studies, Oxaliplatin Injection may impair fertility in males and females [see Nonclinical Toxicology (13.1)].

8.4 Pediatric Use

The safety and effectiveness of Oxaliplatin Injection in pediatrics have not been established. Safety and effectiveness were assessed across 4 open-label studies in 235 patients aged 7 months to 22 years with solid tumors.

In a multicenter, open-label, non-comparative, non-randomized study (ARD5531), oxaliplatin was administered to 43 patients with refractory or relapsed malignant solid tumors, mainly neuroblastoma and osteosarcoma. The dose limiting toxicity (DLT) was sensory neuropathy at a dose of 110 mg/m^2. The main adverse reactions were: paresthesia (60%, grade 3-4: 7%), fever (40%, grade 3-4: 7%), and thrombocytopenia (40%, grade 3-4: 27%). No responses were observed.

In an open-label non-randomized study (DFI7434), oxaliplatin was administered to 26 pediatric patients with metastatic or unresectable solid tumors, mainly neuroblastoma and ganglioneuroblastoma. The DLT was sensory neuropathy at a dose of 160 mg/m^2. No responses were observed.

In an open-label, single-agent study (ARD5021), oxaliplatin was administered to 43 pediatric patients with recurrent or refractory embryonal CNS tumors. The most common adverse reactions reported were: leukopenia (67%, grade 3-4: 12%), anemia (65%, grade 3-4: 5%), thrombocytopenia (65%, grade 3-4: 26%), vomiting (65%, grade 3-4: 7%), neutropenia (58%, grade 3-4: 16%), and sensory neuropathy (40%, grade 3-4: 5%).

In an open-label single-agent study (ARD5530), oxaliplatin was administered to 123 pediatric patients with recurrent solid tumors, including neuroblastoma, osteosarcoma, Ewing sarcoma or peripheral PNET, ependymoma, rhabdomyosarcoma, hepatoblastoma, high grade astrocytoma, brain stem glioma, low grade astrocytoma, malignant germ cell tumor and other tumors. The most common adverse reactions reported were: sensory neuropathy (52%, grade 3-4: 12%), thrombocytopenia (37%, grade 3-4: 17%), anemia (37%, grade 3-4: 9%), vomiting (26%, grade 3-4: 4%), increased ALT (24%, grade 3-4: 6%), increased AST (24%, grade 3-4: 2%), and nausea (23%, grade 3-4: 3%).

The pharmacokinetic parameters of ultrafiltrable platinum were evaluated in 105 pediatric patients during the first cycle. The mean clearance in pediatric patients estimated by the population pharmacokinetic analysis was 4.7 L/h (%CV, 41%). Mean platinum pharmacokinetic parameters in ultrafiltrate were Cmax of 0.75 ± 0.24 mcg/mL, AUC0-48h of 7.52 ± 5.07 mcg•h/mL and AUCinf of 8.83 ± 1.57 mcg•h/mL at 85 mg/m^2 of oxaliplatin and Cmax of 1.10 ± 0.43 mcg/mL, AUC0-48h of 9.74 ± 2.52 mcg•h/mL and AUCinf of 17.3 ± 5.34 mcg•h/mL at 130 mg/m^2 of oxaliplatin.

8.5 Geriatric Use

In the adjuvant treatment trial [see Clinical Studies (14.1)], 400 patients who received oxaliplatin with fluorouracil/leucovorin were greater than or equal to 65 years. The effect of oxaliplatin in patients greater than or equal to 65 years was not conclusive. Patients greater than or equal to 65 years receiving oxaliplatin experienced more diarrhea and grade 3-4 neutropenia (45% vs 39%) compared to patients less than 65 years.

In the previously untreated advanced colorectal cancer trial [see Clinical Studies (14.2)], 99 patients who received oxaliplatin with fluorouracil and leucovorin were greater than or equal to 65 years. The same efficacy improvements in response rate, time to tumor progression, and overall survival were observed in the greater than or equal to 65 years patients as in the overall study population. Adverse reactions were similar in patients less than 65 and greater than or equal to 65 years, but older patients may have been more susceptible to diarrhea, dehydration, hypokalemia, leukopenia, fatigue, and syncope.

In the previously treated advanced colorectal cancer trial [see Clinical Studies (14.3)], 55 patients who received oxaliplatin with fluorouracil and leucovorin were greater than or equal to 65 years. No overall differences in effectiveness were observed between these patients and younger adults. Adverse reactions were similar in patients less than 65 and greater than or equal to 65 years, but older patients may have been more susceptible to diarrhea, dehydration, hypokalemia, and fatigue.

No significant effect of age on the clearance of ultrafiltrable platinum has been observed [see Clinical Pharmacology (12.3)].

8.6 Patients with Renal Impairment

The AUC of unbound platinum in plasma ultrafiltrate was increased in patients with renal impairment [see Clinical Pharmacology (12.3)]. No dose reduction is recommended for patients with mild (creatinine clearance 50 to 79 mL/min) or moderate (creatinine clearance 30 to 49 mL/min) renal impairment, calculated by Cockcroft-Gault equation. Reduce the dose of Oxaliplatin Injection in patients with severe renal impairment (creatinine clearance less than 30 mL/min) [see Dosage and Administration (2.3)].

10 OVERDOSAGE

The maximum dose of oxaliplatin that has been administered in a single infusion is 825 mg. Several cases of overdoses have been reported with oxaliplatin. Adverse reactions observed following an overdosage were grade 4 thrombocytopenia (less than 25,000/mm^3) without bleeding, anemia, sensory neuropathy (including paresthesia, dysesthesia, laryngospasm and facial muscle spasms), gastrointestinal disorders (including nausea, vomiting, stomatitis, flatulence, abdomen enlarged and grade 4 intestinal obstruction), grade 4 dehydration, dyspnea, wheezing, chest pain, respiratory failure, severe bradycardia, and death.

Closely monitor patients suspected of receiving an overdose, including for the adverse reactions described above and administer appropriate supportive treatment.

11 DESCRIPTION

Oxaliplatin is a platinum-based drug with the chemical name of cis-[(1 R,2 R)-1,2-cyclohexanediamine-N,N'] [oxalato(2-)- O,O'] platinum. Oxaliplatin is an organoplatinum complex in which the platinum atom is complexed with 1,2-diaminocyclohexane (DACH) and with an oxalate ligand as a leaving group.

C8H14N2O4Pt

The molecular weight is 397.3. Oxaliplatin is slightly soluble in water at 6 mg/mL, very slightly soluble in methanol, and practically insoluble in ethanol and acetone.

Oxaliplatin Injection for intravenous use is supplied in a single-dose vial containing 50 mg or 100 mg of oxaliplatin as a sterile, preservative-free, aqueous solution at a concentration of 5 mg/mL. The pH is 4.0 to 6.0. Lactose monohydrate is present as an inactive ingredient at 450 mg and 900 mg in the 50 mg and 100 mg dosage strengths, respectively. Water for Injection, USP is also present as an inactive ingredient.

12 CLINICAL PHARMACOLOGY

12.1 Mechanism of Action

Oxaliplatin undergoes nonenzymatic conversion in physiologic solutions to active derivatives via displacement of the labile oxalate ligand. Several transient reactive species are formed, including monoaquo and diaquo DACH platinum, which covalently bind with macromolecules. Both inter- and intrastrand Pt-DNA crosslinks are formed. Crosslinks are formed between the N7 positions of two adjacent guanines (GG), adjacent adenine-guanines (AG), and guanines separated by an intervening nucleotide (GNG). These crosslinks inhibit DNA replication and transcription. Cytotoxicity is cell-cycle nonspecific.

In vivo studies have shown antitumor activity of oxaliplatin against colon carcinoma. In combination with fluorouracil, oxaliplatin exhibits in vitro and in vivo antiproliferative activity greater than either compound alone in several tumor models (HT29 [colon], GR [mammary], and L1210 [leukemia]).

12.2 Pharmacodynamics

A pharmacodynamic relationship between platinum ultrafiltrate levels and clinical safety and effectiveness has not been established.

12.3 Pharmacokinetics

The reactive oxaliplatin derivatives are present as a fraction of the unbound platinum in plasma ultrafiltrate. After a single 2-hour intravenous infusion of oxaliplatin at a dose of 85 mg/m^2, pharmacokinetic parameters expressed as ultrafiltrable platinum were Cmax of 0.814 mcg/mL and volume of distribution of 440 L.

Interpatient and intrapatient variability in ultrafiltrable platinum exposure (AUC0-48hr) assessed over 3 cycles was 23% and 6%, respectively.

Distribution

At the end of a 2-hour infusion of oxaliplatin, approximately 15% of the administered platinum is present in the systemic circulation. The remaining 85% is rapidly distributed into tissues or eliminated in the urine. The decline of ultrafiltrable platinum levels following oxaliplatin administration is triphasic, including two distribution phases (t1/2α; 0.43 hours and t1/2β; 16.8 hours).

In patients, plasma protein binding of platinum is irreversible and is greater than 90%. The main binding proteins are albumin and gamma-globulins.

Platinum also binds irreversibly and accumulates (approximately 2-fold) in erythrocytes, where it appears to have no relevant activity. No platinum accumulation was observed in plasma ultrafiltrate following 85 mg/m^2 every two weeks.

Elimination

The decline of ultrafiltrable platinum concentrations from plasma is characterized by a long terminal elimination phase (t1/2γ; 391 hour).

Metabolism

Oxaliplatin undergoes rapid and extensive nonenzymatic biotransformation. There is no evidence of cytochrome P450-mediated metabolism in vitro.

Up to 17 platinum-containing derivatives have been observed in plasma ultrafiltrate samples from patients, including several cytotoxic species (monochloro DACH platinum, dichloro DACH platinum, and monoaquo and diaquo DACH platinum) and a number of noncytotoxic, conjugated species.

Excretion

The major route of platinum elimination is renal excretion. At five days after a single 2-hour infusion of oxaliplatin, urinary elimination accounted for about 54% of the platinum eliminated, with fecal excretion accounting for only about 2%. Platinum was cleared from plasma at a rate (10 to 17 L/h) that was similar to or exceeded the average human glomerular filtration rate (GFR; 7.5 L/h). The renal clearance of ultrafiltrable platinum is significantly correlated with GFR.

Special Populations

Sex

There was no significant effect of sex on the clearance of ultrafiltrable platinum.

Patients with renal impairment

Patients with normal function (CLcr greater than 80 mL/min) and patients with mild (CLcr=50 to 80 mL/min) and moderate (CLcr equal to 30 to 49 mL/min) renal impairment received oxaliplatin 85 mg/m^2 and those with severe (CLcr less than 30 mL/min) renal impairment received oxaliplatin 65 mg/m^2. Mean dose adjusted AUC of unbound platinum was 40%, 95%, and 342% higher for patients with mild, moderate, and severe renal impairment, respectively, compared to patients with normal renal function. Mean dose adjusted Cmax of unbound platinum appeared to be similar among the normal, mild and moderate renal function groups, but was 38% higher in the severe group than in the normal group [see Dosage and Administration (2.3)].

Drug Interaction Studies

No pharmacokinetic interaction between oxaliplatin 85 mg/m^2 and infusional fluorouracil has been observed in patients treated every 2 weeks, but increases of fluorouracil plasma concentrations by approximately 20% have been observed with doses of 130 mg/m^2 of oxaliplatin administered every 3 weeks.

In vitro platinum was not displaced from plasma proteins by the following medications: erythromycin, salicylate, sodium valproate, granisetron, and paclitaxel.

In vitro oxaliplatin does not inhibit human cytochrome P450 isoenzymes.

13 NONCLINICAL TOXICOLOGY

13.1 Carcinogenesis, Mutagenesis, Impairment of Fertility

Long-term animal studies have not been performed to evaluate the carcinogenic potential of oxaliplatin. Oxaliplatin was not mutagenic to bacteria (Ames test) but was mutagenic to mammalian cells in vitro (L5178Y mouse lymphoma assay). Oxaliplatin was clastogenic both in vitro (chromosome aberration in human lymphocytes) and in vivo (mouse bone marrow micronucleus assay).

In a fertility study, male rats were given oxaliplatin at 0, 0.5, 1, or 2 mg/kg/day for five days every 21 days for a total of three cycles prior to mating with females that received two cycles of oxaliplatin on the same schedule. A dose of 2 mg/kg/day (less than one-seventh the recommended human dose on a body surface area basis) did not affect pregnancy rate, but resulted in 97% postimplantation loss (increased early resorptions, decreased live fetuses, decreased live births), and delayed growth (decreased fetal weight).

Testicular damage, characterized by degeneration, hypoplasia, and atrophy, was observed in dogs administered oxaliplatin at 0.75 mg/kg/day (approximately one-sixth of the recommended human dose on a body surface area basis) x 5 days every 28 days for three cycles. A no effect level was not identified.

14 CLINICAL STUDIES

14.1 Adjuvant Treatment with Oxaliplatin in Combination with Fluorouracil and Leucovorin

The efficacy of oxaliplatin in combination with fluorouracil (FU)/leucovorin (LV) was evaluated in an international, multicenter, randomized (1:1) trial (The Multicenter International Study of Oxaliplatin/5-Fluorouracil/Leucovorin in the Adjuvant Treatment of Colon Cancer [MOSAIC], NCT00275210) in patients with stage II (Dukes’ B2) or III (Dukes’ C) colon cancer who had undergone complete resection of the primary tumor. Patients were randomized to receive oxaliplatin with fluorouracil/leucovorin or fluorouracil/leucovorin alone for a total of 6 months (i.e., 12 cycles). Table 14 shows the dosing regimens for the two arms.

Eligible patients were between 18 and 75 years of age, had histologically proven stage II (T3 to T4 N0 M0; Dukes’ B2) or III (any T N1-2 M0; Dukes’ C) colon carcinoma (with the inferior pole of the tumor above the peritoneal reflection, i.e., greater than or equal to 15 cm from the anal margin) and had undergone (within 7 weeks prior to randomization) complete resection of the primary tumor without gross or microscopic evidence of residual disease and carcino-embyrogenic antigen (CEA) less than 10 ng/mL. Additional eligibility criteria were no prior chemotherapy, immunotherapy or radiotherapy; Eastern Cooperative Oncology Group performance status of 0, 1, or 2 (Karnofsky Performance Status greater than or equal to 60%); no pre-existing neuropathy; and absolute neutrophil count (ANC) greater than or equal to 1.5 × 10^9/L, platelets greater than or equal to 100 × 10^9/L, serum creatinine less than or equal to 1.25 × upper limit normal (ULN), total bilirubin less than 2 × ULN, and aspartate transaminase (AST)/alanine transaminase (ALT) less than 2 × ULN. The major efficacy outcome was 3-year disease-free survival (DFS).

Table 14: Dosing Regimens in Adjuvant Treatment Study
Treatment Arm | Dose | Regimen
Oxaliplatin +; FU/LV; (FOLFOX4); (N = 1123) | Day 1: Oxaliplatin: 85 mg/m^2 (2-hour infusion) + LV: 200 mg/m^2 (2-hour infusion), followed by FU: 400 mg/m^2 (bolus), 600 mg/m^2 (22-hour infusion); Day 2: LV: 200 mg/m^2 (2-hour infusion), followed by FU: 400 mg/m^2 (bolus), 600 mg/m^2 (22-hour infusion) | every 2 weeks; 12 cycles
FU/LV; (N = 1123) | Day 1: LV: 200 mg/m^2 (2-hour infusion), followed by FU: 400 mg/m^2 (bolus), 600 mg/m^2 (22-hour infusion); Day 2: LV: 200 mg/m^2 (2-hour infusion), followed by FU: 400 mg/m^2 (bolus), 600 mg/m^2 (22-hour infusion) | every 2 weeks; 12 cycles

There were 2246 patients enrolled, of whom 1347 (60%) had Stage III disease. Tables 15 and 16 show the baseline characteristics and exposure to oxaliplatin.

Table 15: Baseline Characteristics in Adjuvant Treatment Study
 | Oxaliplatin +; Infusional FU/LV; N = 1123 | Infusional FU/LV; N = 1123
Sex: Male (%) | 56.1 | 52.4
Female (%) | 43.9 | 47.6
Median age (years) | 61.0 | 60.0
< 65 years of age (%) | 64.4 | 66.2
≥ 65 years of age (%) | 35.6 | 33.8
KPS (%)
100 | 29.7 | 30.5
90 | 52.2 | 53.9
80 | 4.4 | 3.3
70 | 13.2 | 11.9
≤ 60 | 0.6 | 0.4
Primary site (%)
Colon including cecum | 54.6 | 54.4
Sigmoid | 31.9 | 33.8
Recto sigmoid | 12.9 | 10.9
Other including rectum | 0.6 | 0.9
Bowel obstruction (%)
Yes | 17.9 | 19.3
Perforation (%)
Yes | 6.9 | 6.9
Stage at Randomization (%)
II (T = 3,4 N = 0, M = 0) | 40.1 | 39.9
III (T = any, N = 1,2, M = 0) | 59.6 | 59.3
IV (T = any, N = any, M = 1) | 0.4 | 0.8
Staging – T (%)
T1 | 0.5 | 0.7
T2 | 4.5 | 4.8
T3 | 76.0 | 75.9
T4 | 19.0 | 18.5
Staging – N (%)
N0 | 40.2 | 39.9
N1 | 39.4 | 39.4
N2 | 20.4 | 20.7
Staging – M (%)
M1 | 0.4 | 0.8

Table 16: Exposure to Oxaliplatin in Adjuvant Treatment Study
 | Oxaliplatin +; Infusional FU/LV; N = 1108 | Infusional FU/LV; N = 1111
Median Relative Dose Intensity (%)
FU | 84.4 | 97.7
Oxaliplatin | 80.5 | N/A
Median Number of Cycles | 12 | 12
Median Number of Cycles with Oxaliplatin | 11 | N/A

The median duration of follow-up was approximately 77 months. In the overall and the stage III colon cancer populations, DFS was statistically significantly improved in the oxaliplatin-containing arm compared to fluorouracil/leucovorin alone; however, a statistically significant improvement in DFS was not observed in Stage II patients. No significant differences in overall survival (OS) were detected in the overall population or those with Stage III disease. Table 17 and Figures 1 and 2 summarize the 5-year DFS rates in the overall randomized population and in patients with stage II and III disease based on an intention-to-treat (ITT) analysis.

Table 17: Summary of DFS Analysis in Adjuvant Treatment Study – ITT Population
Parameter | Oxaliplatin +; Infusional FU/LV | Infusional; FU/LV
Overall
Number of patients | 1123 | 1123
Number of events – relapse or death (%) | 304 (27.1) | 360 (32.1)
5-yr Disease-free survival % (95% CI) | 73.3 (70.7, 76.0) | 67.4 (64.6, 70.2)
Hazard ratio (95% CI) | 0.80 (0.68, 0.93)
Stratified Log rank test | p = 0.003
Stage III (Dukes' C)
Number of patients | 672 | 675
Number of events – relapse or death (%) | 226 (33.6) | 271 (40.1)
5-yr Disease-free survival % (95% CI) | 66.4 (62.7, 70.0) | 58.9 (55.2, 62.7)
Hazard ratio (95% CI) | 0.78 (0.65, 0.93)
Log rank test | p = 0.005
Stage II (Dukes' B2)
Number of patients | 451 | 448
Number of events – relapse or death (%) | 78 (17.3) | 89 (19.9)
5-yr Disease-free survival % (95% CI) | 83.7 (80.2, 87.1) | 79.9 (76.2, 83.7)
Hazard ratio (95% CI) | 0.84 (0.62, 1.14)
Log rank test | p = 0.258
A hazard ratio of less than 1 favors Oxaliplatin + Infusional FU/LV
Data cut off for disease-free survival June 1, 2006

Figure 1: Kaplan-Meier Curves of Disease-Free Survival (cutoff: 1 June 2006) in Adjuvant Treatment Trial – ITT Population

Figure 2: Kaplan-Meier Curves of Disease-Free Survival in Stage III Patients (cutoff: 1 June 2006) in Adjuvant Treatment Trial – ITT Population

Table 18 summarizes the OS results in the overall randomized population and in patients with stage II and III disease, based on the ITT analysis.

Table 18: Summary of OS Analysis in Adjuvant Treatment – ITT Population
Parameter | Oxaliplatin +; Infusional FU/LV | Infusional; FU/LV
Overall
Number of patients | 1123 | 1123
Number of death events (%) | 245 (21.8) | 283 (25.2)
Hazard ratio (95% CI) | 0.84 (0.71, 1.00)
Stage III (Dukes' C)
Number of patients | 672 | 675
Number of death events (%) | 182 (27.1) | 220 (32.6)
Hazard ratio (95% CI) | 0.80 (0.65, 0.97)
Stage II (Dukes' B2)
Number of patients | 451 | 448
Number of death events (%) | 63 (14.0) | 63 (14.1)
Hazard ratio (95% CI) | 1.00 (0.70, 1.41)
A hazard ratio of less than 1 favors oxaliplatin + Infusional FU/LV
Data cut off for overall survival January 16, 2007

14.2 Previously Untreated Advanced Colorectal Cancer

The efficacy of oxaliplatin in combination with fluorouracil (FU)/leucovorin (LV) was evaluated in a North American, multicenter, open-label, randomized, active-controlled trial (A Randomized Phase III Trial of Three Different Regimens of CPT-11 Plus 5-Fluorouracil and Leucovorin Compared to 5-Fluorouracil and Leucovorin in Patients with Advanced Adenocarcinoma of the Colon and Rectum; NCT00003594). The trial included 7 arms at different times during its conduct, four of which were closed due to either changes in the standard of care, toxicity, or simplification. During the trial, the control arm was changed to irinotecan with fluorouracil/leucovorin.

The results reported below compared the efficacy of oxaliplatin with fluorouracil/leucovorin and oxaliplatin with irinotecan to an approved control regimen of irinotecan with fluorouracil/leucovorin in 795 concurrently randomized patients previously untreated for locally advanced or metastatic colorectal cancer. Table 19 presents the dosing regimens for the three arms. After completion of enrollment, the dose of irinotecan with fluorouracil/leucovorin was decreased due to toxicity.

Eligible patients were at least 18 years of age; had known locally advanced, locally recurrent, or metastatic colorectal adenocarcinoma not curable by surgery or amenable to radiation therapy; with an Eastern Cooperative Oncology Group (ECOG) performance status ≤0, 1, or 2. Patients had to have absolute neutrophil count (ANC) greater than or equal to 1.5 × 10^9/L, platelets greater than or equal to 100 × 10^9/L, hemoglobin greater than or equal to 9.0 g/dL, creatinine less than or equal to 1.5 × upper limit of normal (ULN), total bilirubin less than or equal to 1.5 mg/dL, aspartate transaminase (AST) less than or equal to 5 × ULN, and alkaline phosphatase less than or equal to 5 × ULN. Patients may have received adjuvant treatment for resected Stage II or III disease without recurrence within 12 months. Randomization was stratified by ECOG performance status (0, 1 vs 2), prior adjuvant chemotherapy (yes vs no), prior immunotherapy (yes vs no), and age (less than 65 vs greater than or equal to 65 years). Although no post study treatment was specified in the protocol, 65% to 72% of patients received additional post study chemotherapy after study treatment discontinuation on all arms. Fifty-eight percent of patients on the oxaliplatin with fluorouracil/leucovorin arm received an irinotecan-containing regimen and 23% of patients on the irinotecan with fluorouracil/leucovorin arm received an oxaliplatin-containing regimen. The main efficacy outcome measure was 3-year disease-free survival (DFS) and additional efficacy outcome measures were overall survival (OS).

Table 19: Dosing Regimens for Previously Untreated Advanced Colorectal Cancer Clinical Trial
Treatment Arm | Dose | Regimen
Oxaliplatin + FU/LV; (FOLFOX4); (N = 267) | Day 1: Oxaliplatin: 85 mg/m^2 (2-hour infusion) + LV 200 mg/m^2 (2-hour infusion), followed by FU: 400 mg/m^2 (bolus), 600 mg/m^2 (22-hour infusion); Day 2: LV 200 mg/m^2 (2-hour infusion), followed by FU: 400 mg/m^2 (bolus), 600 mg/m^2 (22-hour infusion) | every 2 weeks
Irinotecan +; FU/LV; (IFL); (N = 264) | Day 1: irinotecan 125 mg/m^2 as a 90-min infusion + LV 20 mg/m^2 as a 15-min infusion or intravenous push, followed by FU 500 mg/m^2 intravenous bolus weekly × 4 | every 6 weeks
Oxaliplatin + Irinotecan; (IROX); (N = 264) | Day 1: Oxaliplatin: 85 mg/m^2 intravenous (2-hour infusion) + irinotecan 200 mg/m^2 intravenous over 30 minutes | every 3 weeks

Table 20 presents the baseline characteristics.

Table 20: Baseline Characteristics for Previously Untreated Advanced Colorectal Cancer Clinical Trial
 | Oxaliplatin +; FU/LV; N = 267 | Irinotecan +; FU/LV; N = 264 | Oxaliplatin +; Irinotecan; N = 264
Sex: Male (%) | 58.8 | 65.2 | 61.0
Female (%) | 41.2 | 34.8 | 39.0
Median age (years) | 61.0 | 61.0 | 61.0
< 65 years of age (%) | 61 | 62 | 63
≥ 65 years of age (%) | 39 | 38 | 37
ECOG (%)
0 to 1 | 94.4 | 95.5 | 94.7
2 | 5.6 | 4.5 | 5.3
Involved organs (%)
Colon only | 0.7 | 0.8 | 0.4
Liver only | 39.3 | 44.3 | 39.0
Liver + other | 41.2 | 38.6 | 40.9
Lung only | 6.4 | 3.8 | 5.3
Other (including lymph nodes) | 11.6 | 11.0 | 12.9
Not reported | 0.7 | 1.5 | 1.5
Prior radiation (%) | 3.0 | 1.5 | 3.0
Prior surgery (%) | 74.5 | 79.2 | 81.8
Prior adjuvant (%) | 15.7 | 14.8 | 15.2

The median number of cycles administered per patient was 10 (23.9 weeks) for the oxaliplatin plus fluorouracil/leucovorin regimen, 4 (23.6 weeks) for the irinotecan plus fluorouracil/leucovorin regimen, and 7 (21.0 weeks) for the oxaliplatin plus irinotecan regimen.

Patients who received oxaliplatin with fluorouracil/leucovorin had a significantly longer time to tumor progression based on investigator assessment, longer OS, and a significantly higher confirmed response rate based on investigator assessment compared to patients who received irinotecan with fluorouracil/leucovorin. Efficacy results are summarized in Table 21 and Figure 3.

Table 21: Efficacy Results for Previously Untreated Advanced Colorectal Cancer Trial
 | Oxaliplatin +; FU/LV; N = 267 | Irinotecan +; FU/LV; N = 264 | Oxaliplatin +; Irinotecan; N = 264
Survival (ITT)
Number of deaths (%) | 155 (58.1) | 192 (72.7) | 175 (66.3)
Median survival (months) | 19.4 | 14.6 | 17.6
Hazard ratio (95% CI)* | 0.65 (0.53, 0.80)† |  | -
P-value | < 0.0001† |  | -
TTP (ITT, investigator assessment)
Percentage of progressors | 82.8 | 81.8 | 89.4
Median TTP (months) | 8.7 | 6.9 | 6.5
Hazard ratio (95% CI)* | 0.74 (0.61, 0.89)† |  | -
P-value | 0.0014† |  | -
Response Rate (investigator assessment)‡
Patients with measurable disease | 210 | 212 | 215
Complete response, N (%) | 13 (6.2) | 5 (2.4) | 7 (3.3)
Partial response, N (%) | 82 (39.0) | 64 (30.2) | 67 (31.2)
Complete and partial response, N (%) | 95 (45.2) | 69 (32.5) | 74 (34.4)
95% CI | (38.5, 52.0) | (26.2, 38.9) | (28.1, 40.8)
P-value | 0.0080† |  | -
* A hazard ratio of less than 1 favors ELOXATIN + Infusional FU/LV
† Compared to irinotecan plus fluorouracil/leucovorin (IFL) arm
‡ Based on all patients with measurable disease at baseline
The numbers in the response rate and TTP analysis are based on unblinded investigator assessment.

Figure 3: Kaplan-Meier Curves for Overall Survival in Previously Untreated Advanced Colorectal Cancer Trial

In descriptive subgroup analyses, the improvement in overall survival (OS) for oxaliplatin with fluorouracil/leucovorin compared to irinotecan with fluorouracil/leucovorin appeared to be maintained across age groups, prior adjuvant treatment, number of organs involved and both sexes; however, the effect appeared larger among women than men.

14.3 Previously Treated Advanced Colorectal Cancer

The efficacy of oxaliplatin in combination with fluorouracil (FU)/leucovorin (LV) was evaluated in a multicenter, open-label, randomized, three-arm controlled trial was conducted in the US and Canada in patients with advanced colorectal cancer who had relapsed/progressed during or within 6 months of first-line treatment with bolus fluorouracil/leucovorin and irinotecan (A multicenter, open-label, randomized, three-arm study of 5-fluorouracil (5-FU) + leucovorin (LV) or oxaliplatin or a combination of 5-FU/LV + oxaliplatin as second-line treatment of metastatic colorectal carcinoma: NCT00008281). Patients were randomized to one of three regimens; the dosing regimens are presented in Table 22. Eligible patients were at least 18 years of age, had unresectable, measurable, histologically proven colorectal adenocarcinoma, with a Karnofsky performance status (KPS) greater than 50%. Patients had to have aspartate transaminase (AST), alanine transaminase (ALT) and alkaline phosphatase less than or equal to 2× upper limit of normal (ULN), unless liver metastases were present and documented at baseline by CT or MRI scan, in which case less than or equal to 5× ULN was permitted. Prior radiotherapy was permitted if it had been completed at least 3 weeks before randomization. The main efficacy outcome measure was 3-year disease-free survival (DFS) and an additional outcome measure was overall survival (OS).

Table 22: Dosing Regimens in Refractory and Relapsed Colorectal Cancer Trial
Treatment; Arm | Dose | Regimen
Oxaliplatin; + FU/LV; (N = 152) | Day 1: Oxaliplatin: 85 mg/m^2 (2-hour infusion) + LV 200 mg/m^2 (2-hour infusion), followed by FU: 400 mg/m^2 (bolus), 600 mg/m^2 (22-hour infusion); Day 2: LV 200 mg/m^2 (2-hour infusion), followed by FU: 400 mg/m^2 (bolus), 600 mg/m^2 (22-hour infusion) | every 2 weeks
FU/LV; (N = 151) | Day 1: LV 200 mg/m^2 (2-hour infusion), followed by FU: 400 mg/m^2 (bolus), 600 mg/m^2 (22-hour infusion); Day 2: LV 200 mg/m^2 (2-hour infusion), followed by FU: 400 mg/m^2 (bolus), 600 mg/m^2 (22-hour infusion) | every 2 weeks
Oxaliplatin; (N = 156) | Day 1: Oxaliplatin 85 mg/m^2 (2-hour infusion) | every 2 weeks

Patients must have had at least one unidimensional lesion measuring greater than or equal to 20mm using conventional CT or MRI scans or greater than or equal to 10 mm using a spiral CT scan. Tumor response and progression were assessed every 3 cycles (6 weeks) using the Response Evaluation Criteria in Solid Tumors (RECIST) until radiological documentation of progression or for 13 months following the first dose of study drug(s), whichever came first. Confirmed responses were based on two tumor assessments separated by at least 4 weeks.

Baseline characteristics are shown in Table 23.

Table 23: Baseline Characteristics in Refractory and Relapsed Colorectal Cancer Trial
 | Oxaliplatin + FU/LV N=152 | Oxaliplatin N=156 | FU/LV N=151
Sex: Male (%) | 57.2 | 60.9 | 54.3
Female (%) | 42.8 | 39.1 | 45.7
Median age (years) | 59.0 | 61.0 | 60.0
Range | 22 to 88 | 27 to 79 | 21 to 80
Race (%)
Caucasian | 88.8 | 84.6 | 87.4
Black | 5.9 | 7.1 | 7.9
Asian | 2.6 | 2.6 | 1.3
Other | 2.6 | 5.8 | 3.3
KPS (%)
70 to 100 | 95.4 | 92.3 | 94.7
50 to 60 | 2.0 | 4.5 | 2.6
Not reported | 2.6 | 3.2 | 2.6
Prior radiotherapy (%) | 25.0 | 19.2 | 25.2
Prior pelvic radiation (%) | 21.1 | 13.5 | 18.5
Number of metastatic sites (%)
1 | 25.7 | 31.4 | 27.2
≥2 | 74.3 | 67.9 | 72.2
Liver involvement (%)
Liver only | 18.4 | 25.6 | 22.5
Liver + other | 53.3 | 59.0 | 60.3

The median number of cycles administered per patient was 6 for the oxaliplatin and fluorouracil/leucovorin combination and 3 each for fluorouracil/leucovorin alone and oxaliplatin alone. Patients treated with the combination of oxaliplatin and fluorouracil/leucovorin had an increased response rate compared to patients given fluorouracil/leucovorin or oxaliplatin alone. Efficacy results are summarized in Tables 24 and 25.

Table 24: Response Rates in Refractory and Relapsed Colorectal Cancer Clinical Trial - ITT Analysis
Best Response | Oxaliplatin +; FU/LV N=152 | Oxaliplatin N=156 | FU/LV N=151
Complete Response | 0 | 0 | 0
Partial Response | 13 (9%) | 2 (1%) | 0
P-value | 0.0002 FU/LV vs Oxaliplatin + FU/LV
95% CI | 4.6%, 14.2% | 0.2%, 4.6% | 0, 2.4%

Table 25: Radiographic Time to Progression (TTP)* in Refractory and Relapsed Colorectal Cancer Clinical Trial
Arm | Oxaliplatin + FU/LV N=152 | Oxaliplatin N=156 | FU/LV N=151
Number of progressors | 50 | 101 | 74
Number of patients with no; radiological evaluation beyond baseline | 17 (11%) | 16 (10%) | 22 (15%)
Median TTP (months) | 4.6 | 1.6 | 2.7
95% CI | 4.2, 6.1 | 1.4, 2.7 | 1.8, 3.0
* This is not an ITT analysis. Events were limited to radiographic disease progression documented by independent review of radiographs. Clinical progression was not included in this analysis, and 18% of patients were excluded from the analysis based on unavailability of the radiographs for independent review.

At the time of the interim analysis 49% of the radiographic progression events had occurred. In this interim analysis an estimated 2-month increase in median time to radiographic progression was observed compared to fluorouracil/leucovorin alone.

15 REFERENCES

1. “OSHA Hazardous Drugs.” OSHA. http://www.osha.gov/SLTC/hazardousdrugs/index.html

16 HOW SUPPLIED/STORAGE AND HANDLING

Oxaliplatin Injection is a sterile, preservative-free, aqueous solution for intravenous use supplied as single-dose vials with a gray elastomeric stopper and an aluminum flip-off seal in the following strengths.

NDC 0703-3985-01 50 mg/10 mL (5 mg/mL) individually packaged in a carton

NDC 0703-3986-01 100 mg/20 mL (5 mg/mL) individually packaged in a carton

Store at 20°C to 25°C (68°F to 77°F); excursions permitted to 15°C to 30°C (59°F to 86°F). [See USP Controlled Room Temperature].

DO NOT FREEZE.

PROTECT FROM LIGHT.

Keep in original outer carton. Discard unused portion.

Oxaliplatin Injection is a cytotoxic drug. Follow applicable special handling and disposal procedures.^1 The use of gloves is recommended. If a solution of oxaliplatin contacts the skin, wash the skin immediately and thoroughly with soap and water. If oxaliplatin contacts the mucous membranes, flush thoroughly with water.

17 PATIENT COUNSELING INFORMATION

Hypersensitivity Reactions

Advise patients of the potential risk of hypersensitivity and that oxaliplatin is contraindicated in patients with a history of hypersensitivity reactions to oxaliplatin and other platinum-based drugs. Instruct patients to seek immediate medical attention for signs of severe hypersensitivity reaction such as chest tightness; shortness of breath; wheezing; dizziness or faintness; or swelling of the face, eyelids, or lips [see Warnings and Precautions (5.1)].

Peripheral Sensory Neuropathy

Advise patients of the risk of acute reversible or persistent-type neurosensory toxicity. Advise patients to avoid cold drinks, use of ice, and exposure of skin to cold temperature or cold objects [see Warnings and Precautions (5.2)].

Myelosuppression

Inform patients that oxaliplatin can cause low blood cell counts and the need for frequent monitoring of blood cell counts. Advise patients to contact their healthcare provider immediately for bleeding, fever, particularly if associated with persistent diarrhea, or symptoms of infection develop [see Warnings and Precautions (5.3)].

Posterior Reversible Encephalopathy Syndrome

Advise patients of the potential effects of vision abnormalities, in particular transient vision loss (reversible following therapy discontinuation), which may affect the patients' ability to drive and use machines [see Warnings and Precautions (5.4)].

Pulmonary Toxicity

Advise patients to report immediately to their healthcare provider any persistent or recurrent respiratory symptoms, such as non-productive cough and dyspnea [see Warnings and Precautions (5.5)].

Hepatotoxicity

Advise patients to report signs or symptoms of hepatic toxicity to their healthcare provider [see Warnings and Precautions (5.6)].

QT Interval Prolongation

Advise patients that oxaliplatin can cause QTc interval prolongation and to inform their physician if they have any symptoms, such as syncope [see Warnings and Precautions (5.7)].

Rhabdomyolysis

Advise patients to contact their healthcare provider immediately for new or worsening signs or symptoms of muscle toxicity, dark urine, decreased urine output, or the inability to urinate [see Warnings and Precautions (5.8)].

Hemorrhage

Advise patients that oxaliplatin may increase the risk of bleeding and to promptly inform their healthcare provider of any bleeding episodes [see Warnings and Precautions (5.9)].

Embryo-Fetal Toxicity

Advise females of reproductive potential of the potential risk to a fetus. Advise females to inform their healthcare provider of a known or suspected pregnancy [see Warnings and Precautions (5.10), Use in Specific Populations (8.1)].

Advise females of reproductive potential to use effective contraception during treatment with Oxaliplatin Injection and for 9 months after the final dose [see Use in Specific Populations (8.3)].

Advise male patients with female partners of reproductive potential to use effective contraception during treatment with Oxaliplatin Injection and for 6 months after the final dose [see Use in Specific Populations (8.3), Nonclinical Toxicology (13.1)].

Lactation

Advise women not to breastfeed during treatment with Oxaliplatin Injection and for 3 months after the final dose [see Use in Specific Populations (8.2)].

Infertility

Advise females and males of reproductive potential that Oxaliplatin Injection may impair fertility [see Use in Specific Populations (8.3), Nonclinical Toxicology (13.1)].

Gastrointestinal

Advise patients to contact their healthcare provider for persistent vomiting, diarrhea, or signs of dehydration [see Adverse Reactions (6.1)].

Drug Interactions

Inform patients about the risk of drug interactions and the importance of providing a list of prescription and nonprescription drugs to their healthcare provider [see Drug Interactions (7)].

Manufactured In The Netherlands By:
Pharmachemie B.V.
Haarlem, The Netherlands

Manufactured For:
Teva Pharmaceuticals
Parsippany, NJ 07054

Rev. K 10/2024

Patient Information

OXALIPLATIN (ox al i pla tin)

injection, for intravenous use

What is the most important information I should know about Oxaliplatin Injection?

Oxaliplatin Injection can cause serious allergic reactions, including allergic reactions that can lead to death.

Oxaliplatin Injection is a platinum-based medicine. Serious allergic reactions including death can happen in people who take oxaliplatin and who have had previous allergic reactions to platinum-based medicines. Serious allergic reactions can happen within a few minutes of your Oxaliplatin Injection infusion or any time during your treatment with Oxaliplatin Injection.

Get emergency help right away if you:

- have trouble breathing
- feel like your throat is closing up
- have chest tightness

Call your healthcare provider right away if you have any of the following signs or symptoms of an allergic reaction:

- rash
- flushed face
- hives
- itching
- swelling of your lips or tongue, face or eyelids

- wheezing
- sudden cough
- dizziness or feel faint
- sweating
- chest pain

See "What are the possible side effects of Oxaliplatin Injection?" for information about other serious side effects.

What is Oxaliplatin Injection?

Oxaliplatin Injection is an anti-cancer (chemotherapy) medicine that is used with other anti-cancer medicines called fluorouracil and leucovorin to treat people with:

- stage III colon cancer after surgery to remove the tumor
- advanced colon or rectal cancer (colorectal cancer)

It is not known if Oxaliplatin Injection is safe and effective in children.

Do not receive Oxaliplatin Injection if you have had an allergic reaction to oxaliplatin or if you are allergic to other platinum-based medicines. See the end of this leaflet for a complete list of ingredients in Oxaliplatin Injection.
Ask your healthcare provider if you are not sure if you have taken a platinum-based medicine.

Before receiving Oxaliplatin Injection, tell your healthcare provider about all of your medical conditions, including if you:

- have an infection
- have lung, liver, or kidney problems
- have bleeding problems
- have or had heart problems such as an abnormal heart test called an electrocardiogram (ECG or EKG), a condition called long QT syndrome, an irregular or slow heartbeat, or a family history of heart problems
- have had changes in the level of certain blood salt (electrolytes) levels, including potassium, magnesium, and calcium
- are pregnant or plan to become pregnant. Oxaliplatin Injection can harm your unborn baby. Tell your healthcare provider right away if you become pregnant or think you may be pregnant during treatment with Oxaliplatin Injection.
  Females who are able to become pregnant:
  - Your healthcare provider will do a pregnancy test before you start treatment with Oxaliplatin Injection.
  - You should use effective birth control (contraception) during treatment with Oxaliplatin Injection and for 9 months after the final dose. Talk to your healthcare provider about forms of birth control that may be right for you.
  Males with female partners who are able to become pregnant should use effective birth control during treatment with Oxaliplatin Injection and for 6 months after the final dose.
- are breastfeeding or plan to breastfeed. It is not known if Oxaliplatin Injection passes into your breast milk. Do not breastfeed during treatment with Oxaliplatin Injection and for 3 months after the final dose.

Tell your healthcare provider about all the medicines you take, including prescription and over-the-counter medicines, vitamins, and herbal supplements.

Know the medicines you take. Keep a list of them and show it to your healthcare provider and pharmacist when you get a new medicine.

How will I receive Oxaliplatin Injection?

- Oxaliplatin Injection is given to you into your vein through an intravenous (IV) tube.
- Your healthcare provider will prescribe Oxaliplatin Injection in a dose that is right for you.
- Your healthcare provider may change how often you receive Oxaliplatin Injection, your dose, or how long your infusion will take.
- You and your healthcare provider will decide how many Oxaliplatin Injection treatments you will receive.
- It is very important that you do exactly what your healthcare provider tells you to do.
- Some medicines may be given to you before Oxaliplatin Injection to help prevent nausea and vomiting.
- Each treatment course is given to you over 2 days. You will receive Oxaliplatin Injection on the first day only.
- There are usually 14 days (2 weeks) between each chemotherapy treatment course.
- It is important for you to keep all of your medical appointments. Call your healthcare provider if you miss an appointment. There may be special instructions for you.

Treatment Day 1:

- Oxaliplatin Injection and leucovorin will be given through a thin plastic tube into a vein (intravenous infusion or IV) and given for 2 hours. You will be watched by a healthcare provider during this time.
- Right after the Oxaliplatin Injection and leucovorin are given, 2 doses of fluorouracil will be given. The first dose is given right away into your IV tube. The second dose will be given into your IV tube over the next 22 hours, using a pump device.

Treatment Day 2:

You will not get Oxaliplatin Injection on Day 2. Leucovorin and fluorouracil will be given the same way as on Day 1.

The fluorouracil will be given through your IV with a pump. If you have any problems with the pump or the tube, call your healthcare provider or the person who is responsible for your pump. Do not let anyone other than a healthcare provider touch your infusion pump or tubing.

What should I avoid while receiving Oxaliplatin Injection?

- Avoid cold temperatures and cold objects. Cover your skin if you go outdoors in cold temperatures.
- Do not drink cold drinks or use ice cubes in drinks.
- Do not put ice or ice packs on your body.
- Oxaliplatin Injection can cause dizziness, vision problems, or vision loss that can affect your ability to drive or use machines. You should not drive or operate machinery if you develop these symptoms while receiving Oxaliplatin Injection.

See “How can I reduce the side effects caused by cold temperatures?” for more information.

Talk with your healthcare provider about your level of activity during treatment with Oxaliplatin Injection. Follow their instructions.

What are the possible side effects of Oxaliplatin Injection?

Oxaliplatin Injection can cause serious side effects, including:

- See “What is the most important information I should know about Oxaliplatin Injection?”
- Nerve problems. Oxaliplatin Injection can affect how your nerves work and make you feel. Nerve problems may happen with the first treatment or within 2 days after your treatment with Oxaliplatin Injection. Nerve problems may last a short time (acute) or may become persistent. Symptoms may improve after stopping treatment with Oxaliplatin Injection. Exposure to cold or cold objects may cause or worsen nerve problems. Tell your healthcare provider right away if you get any signs of nerve problems, including:
  - very sensitive to cold temperatures and cold objects
  - trouble breathing, swallowing, or saying words, jaw tightness, odd feelings in your tongue, or chest pressure
  - pain, tingling, burning (pins and needles, numb feeling) in your hands, feet, or around your mouth or throat, which may cause problems walking, fall and fall-related injuries, or problems performing activities of daily living

For information on ways to lessen or help with nerve problems, see the section “How can I reduce the side effects caused by cold temperatures?” below.

- Severe low blood cell counts (myelosuppression). Oxaliplatin Injection when used with fluorouracil and leucovorin can cause low blood cells counts. Low blood cell counts are common with Oxaliplatin Injection when used with fluorouracil and leucovorin and can lead to serious infection and death. Your healthcare provider will do blood tests to check your blood cell counts before starting Oxaliplatin Injection and during treatment. Tell your healthcare provider right away if you have a fever greater than 100.9°F (38.3°C) or a prolonged fever greater than 100.4°F (38°C) for more than 1 hour (febrile neutropenia). Call your healthcare provider right away if you get any of the following signs of infection:

- chills or shivering
- pain on swallowing
- sore throat
- cough that brings up mucus

- burning or pain on urination
- redness or swelling at intravenous site
- persistent diarrhea

- Posterior Reversible Encephalopathy Syndrome (PRES). PRES is a rare condition that affects the brain. Tell your healthcare provider right away if you have any of the following signs and symptoms of PRES:
  - headache
  - confusion or a change in the way you think
  - seizures
  - vision problems, such as blurriness or vision loss
- Lung problems. Oxaliplatin Injection can cause lung problems that may lead to death. Tell your healthcare provider right away if you get any of the following symptoms as these may be indicators of a serious lung disease:

- shortness of breath
- wheezing

- cough

- Liver problems (hepatotoxicity). Your healthcare provider will do blood tests to check your liver when you start receiving Oxaliplatin Injection, and before each treatment course as needed.

- Heart problems. Oxaliplatin Injection can cause heart problems that have led to death. Your healthcare provider may do blood and heart tests during treatment with Oxaliplatin Injection if you have certain heart problems. If you faint (lose consciousness), or have an irregular heartbeat or chest pain during treatment with Oxaliplatin Injection, get medical help right away as this may be a sign of a serious heart condition.
- Muscle problems. Oxaliplatin Injection can cause muscle damage (rhabdomyolysis) which can lead to death. Tell your healthcare provider right away if you have muscle pain and swelling, along with weakness, fever, red-brown urine, decreased amount of urine or trouble urinating.

- Bleeding problems (hemorrhage). Oxaliplatin Injection when used with fluorouracil and leucovorin can cause bleeding problems (hemorrhage) that can lead to death. Your risk of bleeding may increase if you are also taking a blood thinner medicine. Tell your healthcare provider if you have any signs or symptoms of bleeding, including:

- blood in your stools or black stools (looks like tar)
- pink or brown urine
- unexpected bleeding, or bleeding that is severe or you cannot control
- vomit blood or vomit that looks like coffee grounds
- cough up blood or blood clots

- increased bruising
- dizziness
- weakness
- confusion
- changes in speech
- headache that lasts a long time

The most common side effects of Oxaliplatin Injection include:

- numbness, pain, tingling, and burning along the nerves
- low white blood cells (blood cells important for fighting infection)
- low platelet count (important for clotting and to control bleeding)
- low red blood cells (blood cells that carry oxygen to the tissues)
- nausea

- changes in liver function tests
- diarrhea
- vomiting
- tiredness
- mouth sores

Oxaliplatin Injection may cause fertility problems in males and females. Talk to your healthcare provider if this is a concern for you.

Tell your healthcare provider if you have any side effect that bothers you or that does not go away. These are not all the possible side effects of Oxaliplatin Injection. For more information, ask your healthcare provider or pharmacist.

Call your doctor for medical advice about side effects. You may report side effects to FDA at 1-800-FDA-1088.

How can I reduce the side effects caused by cold temperatures?

- Cover yourself with a blanket while you are getting your Oxaliplatin Injection infusion.
- Do not breathe deeply when exposed to cold air.
- Wear warm clothing in cold weather at all times. Cover your mouth and nose with a scarf or a pull-down cap (ski cap) to warm the air that goes to your lungs.
- Wear gloves when taking things from the freezer or refrigerator.
- Drink fluids warm or at room temperature.
- Always drink through a straw.
- Do not use ice chips if you have nausea or mouth sores. Ask your healthcare provider about what you can use.
- Be aware that most metals are cold to touch, especially in the winter. These include your car door and mailbox. Wear gloves to touch cold objects.
- Do not run the air conditioning at high levels in the house or in the car in hot weather.
- If your body gets cold, warm-up the affected part. If your hands get cold, wash them with warm water.
- Always let your healthcare provider know before your next treatment how well you did since your last visit.

Your healthcare provider may have other useful tips for helping you with side effects.

General information about the safe and effective use of Oxaliplatin Injection.

Medicines are sometimes prescribed for purposes other than those listed in the Patient Information leaflet. You can ask your healthcare provider or pharmacist for information about Oxaliplatin Injection that is written for health professionals.

What are the ingredients in Oxaliplatin Injection?
Active ingredient: oxaliplatin
Inactive ingredients: lactose monohydrate and water for injection.

Manufactured In The Netherlands By: Pharmachemie B.V., Haarlem, The Netherlands

Manufactured For: Teva Pharmaceuticals, Parsippany, NJ 07054

This Patient Information has been approved by the U.S. Food and Drug Administration. Revised: K 10/2024

Package/Label Display Panel

NDC 0703-3985-01

Oxaliplatin Injection

50 mg/10 mL
(5 mg/mL)

For Intravenous Use Only

PHARMACIST: Dispense with accompanying patient information leaflet to each patient.

Sterile Aqueous Solution -
Preservative Free

Must Be Diluted Prior to Use with 5% Dextrose Injection

Caution: Contains Cytotoxic Agent

Single-Dose Vial -
Discard Unused Portion

Rx only

Package/Label Display Panel

NDC 0703-3986-01

Oxaliplatin Injection

100 mg/20 mL
(5 mg/mL)

For Intravenous Use Only

PHARMACIST: Dispense with accompanying patient information leaflet to each patient.

Sterile Aqueous Solution -
Preservative Free

Must Be Diluted Prior to Use with 5% Dextrose Injection

Caution: Contains Cytotoxic Agent

Single-Dose Vial -
Discard Unused Portion

Rx only